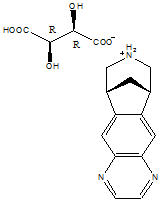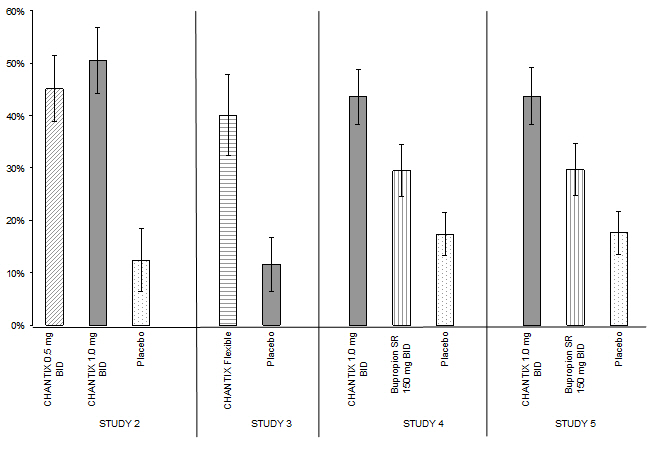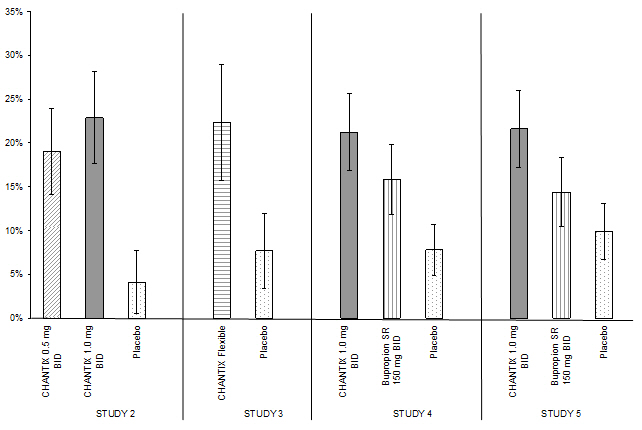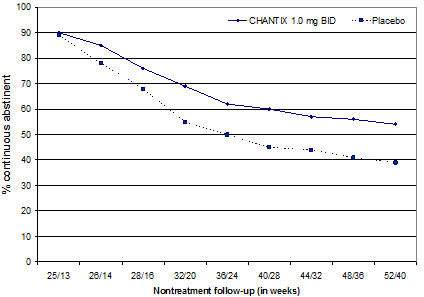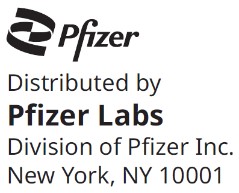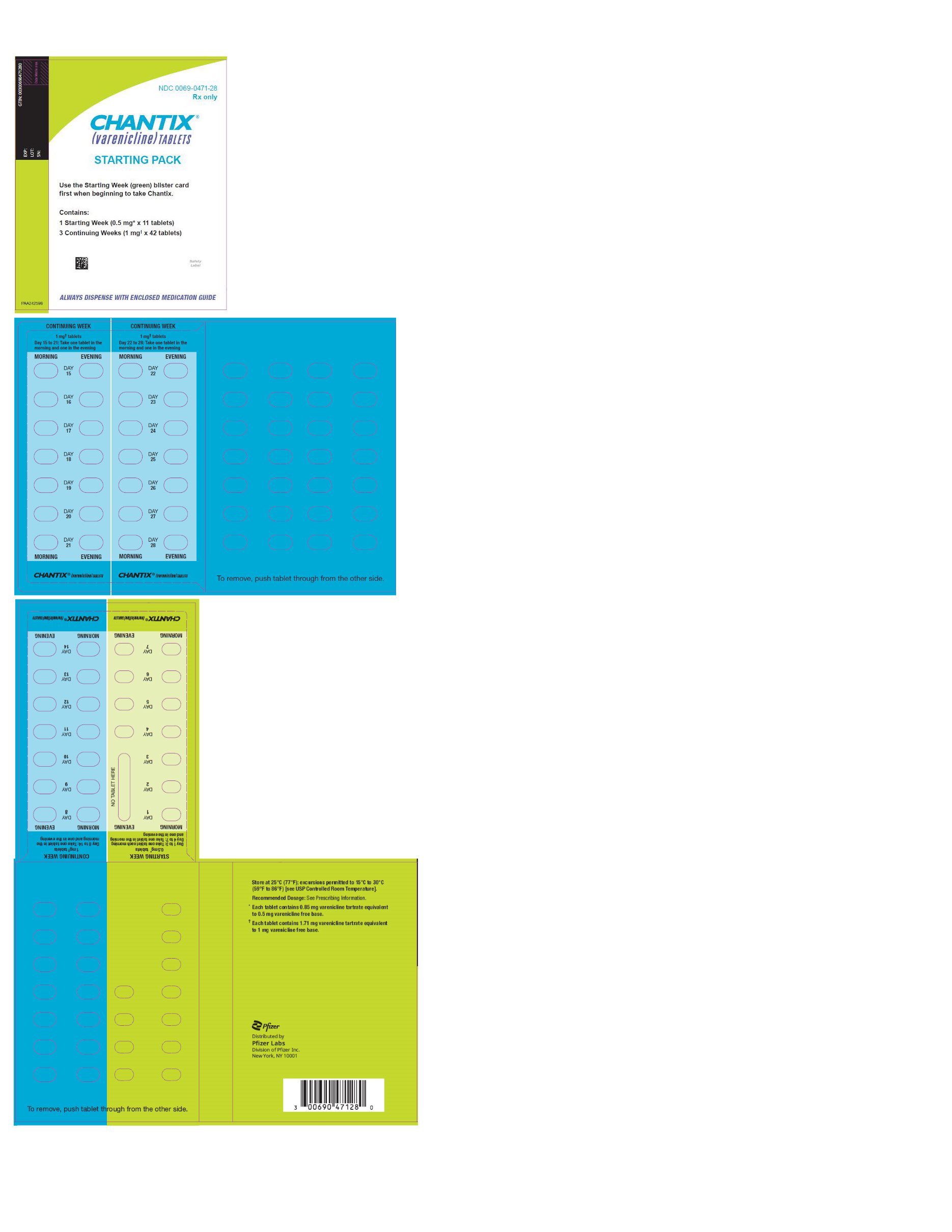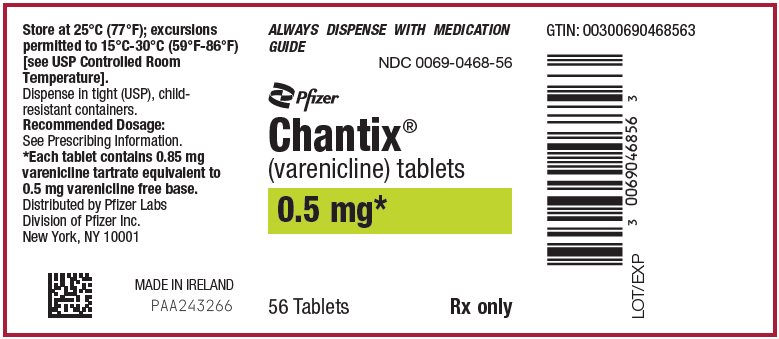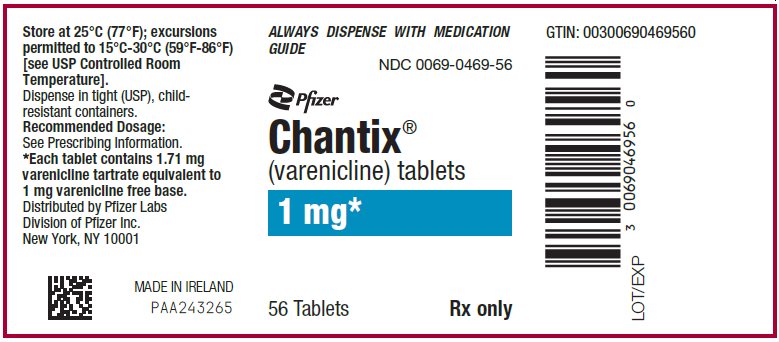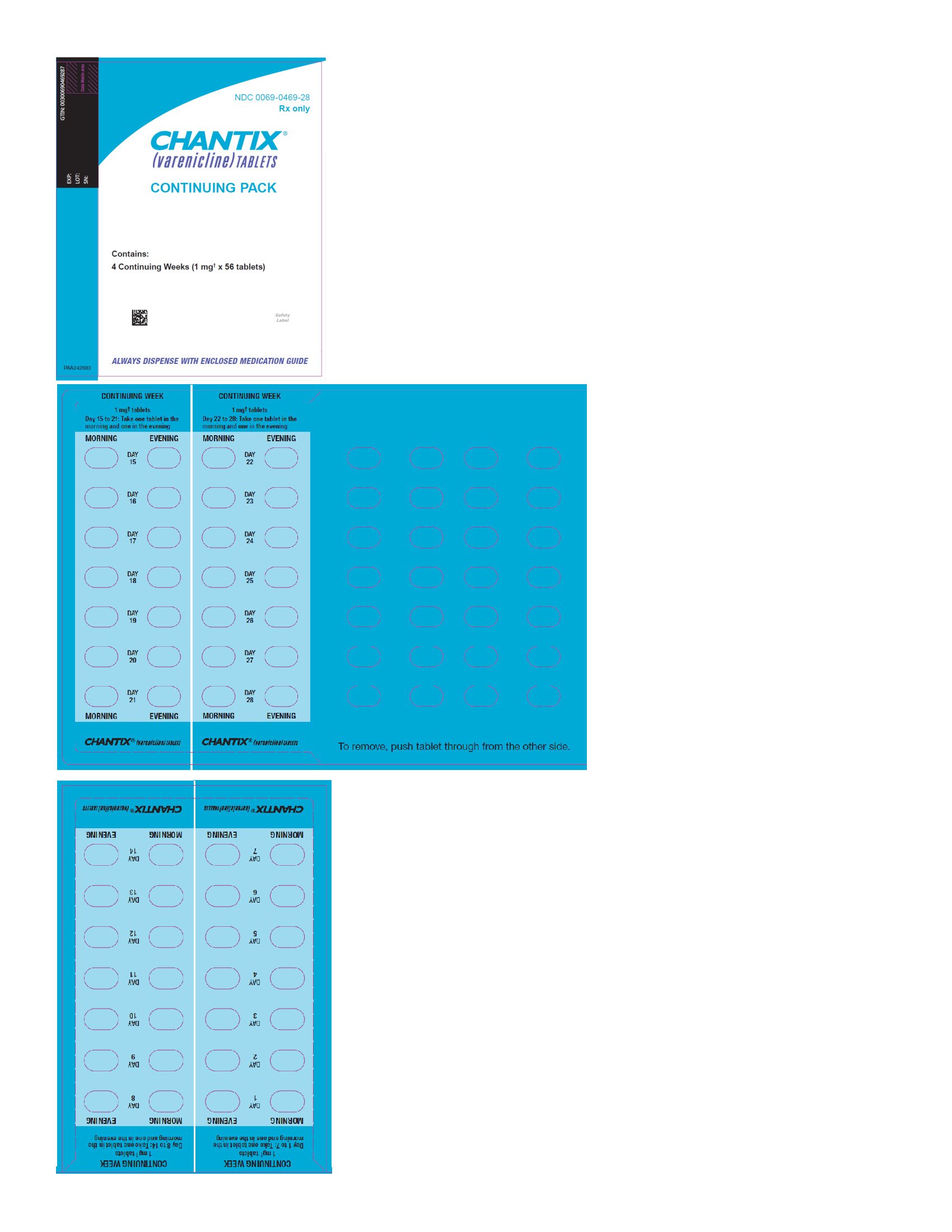 DRUG LABEL: CHANTIX
NDC: 0069-0468 | Form: TABLET, FILM COATED
Manufacturer: Pfizer Laboratories Div Pfizer Inc
Category: prescription | Type: HUMAN PRESCRIPTION DRUG LABEL
Date: 20260123

ACTIVE INGREDIENTS: VARENICLINE TARTRATE 0.5 mg/1 1
INACTIVE INGREDIENTS: MICROCRYSTALLINE CELLULOSE; ANHYDROUS DIBASIC CALCIUM PHOSPHATE; CROSCARMELLOSE SODIUM; SILICON DIOXIDE; MAGNESIUM STEARATE; HYPROMELLOSE, UNSPECIFIED; TITANIUM DIOXIDE; POLYETHYLENE GLYCOL, UNSPECIFIED; TRIACETIN; FD&C BLUE NO. 2

HIGHLIGHTS OF PRESCRIBING INFORMATION

These highlights do not include all the information needed to use CHANTIX safely and effectively. See full prescribing information for CHANTIX.
CHANTIX® (varenicline) tablets, for oral use
Initial U.S. Approval: 2006

1 INDICATIONS AND USAGE

CHANTIX is a nicotinic receptor partial agonist indicated for use as an aid to smoking-cessation treatment. (1 and 2.1)

2 DOSAGE AND ADMINISTRATION

- Begin CHANTIX dosing one week before the date set by the patient to stop smoking. Alternatively, the patient can begin CHANTIX dosing and then quit smoking between days 8 and 35 of treatment. (2.1)
- Starting Week: 0.5 mg once daily on days 1–3 and 0.5 mg twice daily on days 4–7. (2.1)
- Continuing Weeks: 1 mg twice daily for a total of 12 weeks. (2.1)
- An additional 12 weeks of treatment is recommended for successful quitters to increase likelihood of long-term abstinence. (2.1)
- Consider a gradual approach to quitting smoking with CHANTIX for patients who are sure that they are not able or willing to quit abruptly. Patients should begin CHANTIX dosing and reduce smoking by 50% from baseline within the first four weeks, by an additional 50% in the next four weeks, and continue reducing with the goal of reaching complete abstinence by 12 weeks. Continue treatment for an additional 12 weeks, for a total of 24 weeks. (2.1)
- Severe Renal Impairment (estimated creatinine clearance less than 30 mL/min): Begin with 0.5 mg once daily and titrate to 0.5 mg twice daily. For patients with end-stage renal disease undergoing hemodialysis, a maximum of 0.5 mg daily may be given if tolerated. (2.2)
- Consider dose reduction for patients who cannot tolerate adverse effects. (2.1)
- Another attempt at treatment is recommended for those who fail to stop smoking or relapse when factors contributing to the failed attempt have been addressed. (2.1)
- Provide patients with appropriate educational materials and counseling to support the quit attempt. (2.1)

3 DOSAGE FORMS AND STRENGTHS

Tablets: 0.5 mg and 1 mg (3)

4 CONTRAINDICATIONS

History of serious hypersensitivity or skin reactions to CHANTIX. (4)

5 WARNINGS AND PRECAUTIONS

- Neuropsychiatric Adverse Events: Postmarketing reports of serious or clinically significant neuropsychiatric adverse events have included changes in mood (including depression and mania), psychosis, hallucinations, paranoia, delusions, homicidal ideation, aggression, hostility, agitation, anxiety, and panic, as well as suicidal ideation, suicide attempt, and completed suicide. Observe patients attempting to quit smoking with CHANTIX for the occurrence of such symptoms and instruct them to discontinue CHANTIX and contact a healthcare provider if they experience such adverse events. (5.1)
- Seizures: New or worsening seizures have been observed in patients taking CHANTIX. CHANTIX should be used cautiously in patients with a history of seizures or other factors that can lower the seizure threshold. (5.2)
- Interaction with Alcohol: Increased effects of alcohol have been reported. Instruct patients to reduce the amount of alcohol they consume until they know whether CHANTIX affects them. (5.3)
- Accidental Injury: Accidental injuries (e.g., traffic accidents) have been reported. Instruct patients to use caution driving or operating machinery until they know how CHANTIX may affect them. (5.4)
- Cardiovascular Events: Patients with underlying cardiovascular (CV) disease may be at increased risk of CV events; however, these concerns must be balanced with the health benefits of smoking cessation. Instruct patients to notify their healthcare providers of new or worsening CV symptoms and to seek immediate medical attention if they experience signs and symptoms of myocardial infarction (MI) or stroke. (5.5 and 6.1)
- Somnambulism: Cases of somnambulism have been reported in patients taking CHANTIX. Some cases described harmful behavior to self, others, or property. Instruct patients to discontinue CHANTIX and notify their healthcare provider if they experience somnambulism. (5.6 and 6.2)
- Angioedema and Hypersensitivity Reactions: Such reactions, including angioedema, infrequently life-threatening, have been reported. Instruct patients to discontinue CHANTIX and immediately seek medical care if symptoms occur. (5.7 and 6.2)
- Serious Skin Reactions: Rare, potentially life-threatening skin reactions have been reported. Instruct patients to discontinue CHANTIX and contact a healthcare provider immediately at first appearance of skin rash with mucosal lesions. (5.8 and 6.2)
- Nausea: Nausea is the most common adverse reaction (up to 30% incidence rate). Dose reduction may be helpful. (5.9)

6 ADVERSE REACTIONS

Most common adverse reactions (>5% and twice the rate seen in placebo-treated patients) were nausea, abnormal (e.g., vivid, unusual, or strange) dreams, constipation, flatulence, and vomiting. (6)

To report SUSPECTED ADVERSE REACTIONS, contact Pfizer Inc. at 1-800-438-1985 or FDA at 1-800-FDA-1088 or www.fda.gov/medwatch.

7 DRUG INTERACTIONS

- Other Smoking-Cessation Therapies: Safety and efficacy in combination with other smoking-cessation therapies has not been established. Coadministration of varenicline and transdermal nicotine resulted in a high rate of discontinuation due to adverse events. (7.1)
- Effect of Smoking Cessation on Other Drugs: Pharmacokinetics or pharmacodynamics of certain drugs (e.g., theophylline, warfarin, insulin) may be altered, necessitating dose adjustment. (7.2)

FULL PRESCRIBING INFORMATION

1 INDICATIONS AND USAGE

CHANTIX is indicated for use as an aid to smoking-cessation treatment.

2 DOSAGE AND ADMINISTRATION

2.1 Recommended Dosage for Adults

Smoking-cessation therapies are more likely to succeed for patients who are motivated to stop smoking and who are provided additional advice and support. Provide patients with appropriate educational materials and counseling to support the quit attempt.

The patient should set a date to stop smoking. Begin CHANTIX dosing one week before this date. Alternatively, the patient can begin CHANTIX dosing and then quit smoking between days 8 and 35 of treatment.

CHANTIX should be taken orally after eating and with a full glass of water.

The recommended dose of CHANTIX is 1 mg twice daily following a 1-week titration as follows:

Days 1 – 3: | 0.5 mg once daily
Days 4 – 7: | 0.5 mg twice daily
Day 8 – end of treatment: | 1 mg twice daily

Patients should be treated with CHANTIX for 12 weeks. For patients who have successfully stopped smoking at the end of 12 weeks, an additional course of 12 weeks treatment with CHANTIX is recommended to further increase the likelihood of long-term abstinence.

For patients who are sure that they are not able or willing to quit abruptly, consider a gradual approach to quitting smoking with CHANTIX. Patients should begin CHANTIX dosing and reduce smoking by 50% from baseline within the first four weeks, by an additional 50% in the next four weeks, and continue reducing with the goal of reaching complete abstinence by 12 weeks. Continue CHANTIX treatment for an additional 12 weeks, for a total of 24 weeks of treatment. Encourage patients to attempt quitting sooner if they feel ready [see Clinical Studies (14.5)].

Patients who are motivated to quit, and who did not succeed in stopping smoking during prior CHANTIX therapy for reasons other than intolerability due to adverse events or who relapsed after treatment, should be encouraged to make another attempt with CHANTIX once factors contributing to the failed attempt have been identified and addressed.

Consider a temporary or permanent dose reduction in patients who cannot tolerate the adverse effects of CHANTIX.

2.2 Dosage in Special Populations

Patients with Impaired Renal Function

No dosage adjustment is necessary for patients with mild-to-moderate renal impairment. For patients with severe renal impairment (estimated creatinine clearance less than 30 mL per min), the recommended starting dose of CHANTIX is 0.5 mg once daily. The dose may then be titrated as needed to a maximum dose of 0.5 mg twice daily. For patients with end-stage renal disease undergoing hemodialysis, a maximum dose of 0.5 mg once daily may be administered if tolerated [see Use in Specific Populations (8.6), Clinical Pharmacology (12.3)].

Elderly and Patients with Impaired Hepatic Function

No dosage adjustment is necessary for patients with hepatic impairment. Because elderly patients are more likely to have decreased renal function, care should be taken in dose selection, and it may be useful to monitor renal function [see Use in Specific Populations (8.5)].

3 DOSAGE FORMS AND STRENGTHS

Capsular, biconvex tablets: 0.5 mg (white to off-white, debossed with "Pfizer" on one side and "CHX 0.5" on the other side) and 1 mg (light blue, debossed with "Pfizer" on one side and "CHX 1.0" on the other side).

4 CONTRAINDICATIONS

CHANTIX is contraindicated in patients with a known history of serious hypersensitivity reactions or skin reactions to CHANTIX.

5 WARNINGS AND PRECAUTIONS

5.1 Neuropsychiatric Adverse Events including Suicidality

Serious neuropsychiatric adverse events have been reported in patients being treated with CHANTIX [see Adverse Reactions (6.2)]. These postmarketing reports have included changes in mood (including depression and mania), psychosis, hallucinations, paranoia, delusions, homicidal ideation, aggression, hostility, agitation, anxiety, and panic, as well as suicidal ideation, suicide attempt, and completed suicide. Some patients who stopped smoking may have been experiencing symptoms of nicotine withdrawal, including depressed mood. Depression, rarely including suicidal ideation, has been reported in smokers undergoing a smoking-cessation attempt without medication. However, some of these adverse events occurred in patients taking CHANTIX who continued to smoke.

Neuropsychiatric adverse events occurred in patients without and with pre-existing psychiatric disease; some patients experienced worsening of their psychiatric illnesses. Some neuropsychiatric adverse events, including unusual and sometimes aggressive behavior directed to oneself or others, may have been worsened by concomitant use of alcohol [see Warnings and Precautions (5.3), Adverse Reactions (6.2)]. Observe patients for the occurrence of neuropsychiatric adverse events. Advise patients and caregivers that the patient should stop taking CHANTIX and contact a healthcare provider immediately if agitation, depressed mood, or changes in behavior or thinking that are not typical for the patient are observed, or if the patient develops suicidal ideation or suicidal behavior. The healthcare provider should evaluate the severity of the symptoms and the extent to which the patient is benefiting from treatment, and consider options including dose reduction, continued treatment under closer monitoring, or discontinuing treatment. In many postmarketing cases, resolution of symptoms after discontinuation of CHANTIX was reported. However, the symptoms persisted in some cases; therefore, ongoing monitoring and supportive care should be provided until symptoms resolve.

The neuropsychiatric safety of CHANTIX was evaluated in a randomized, double-blind, active and placebo-controlled study that included patients without a history of psychiatric disorder (non-psychiatric cohort, N=3912) and patients with a history of psychiatric disorder (psychiatric cohort, N=4003). In the non-psychiatric cohort, CHANTIX was not associated with an increased incidence of clinically significant neuropsychiatric adverse events in a composite endpoint comprising anxiety, depression, feeling abnormal, hostility, agitation, aggression, delusions, hallucinations, homicidal ideation, mania, panic, and irritability. In the psychiatric cohort, there were more events reported in each treatment group compared to the non-psychiatric cohort, and the incidence of events in the composite endpoint was higher for each of the active treatments compared to placebo: Risk Differences (RDs) (95%CI) vs. placebo were 2.7% (-0.05, 5.4) for CHANTIX, 2.2% (-0.5, 4.9) for bupropion, and 0.4% (-2.2, 3.0) for transdermal nicotine. In the non-psychiatric cohort, neuropsychiatric adverse events of a serious nature were reported in 0.1% of CHANTIX-treated patients and 0.4% of placebo-treated patients. In the psychiatric cohort, neuropsychiatric events of a serious nature were reported in 0.6% of CHANTIX-treated patients, with 0.5% involving psychiatric hospitalization. In placebo-treated patients, serious neuropsychiatric events occurred in 0.6%, with 0.2% requiring psychiatric hospitalization [see Clinical Studies (14.10)].

5.2 Seizures

During clinical trials and the postmarketing experience, there have been reports of seizures in patients treated with CHANTIX. Some patients had no history of seizures, whereas others had a history of seizure disorder that was remote or well-controlled. In most cases, the seizure occurred within the first month of therapy. Weigh this potential risk against the potential benefits before prescribing CHANTIX in patients with a history of seizures or other factors that can lower the seizure threshold. Advise patients to discontinue CHANTIX and contact a healthcare provider immediately if they experience a seizure while on treatment [see Adverse Reactions (6.2)].

5.3 Interaction with Alcohol

There have been postmarketing reports of patients experiencing increased intoxicating effects of alcohol while taking CHANTIX. Some cases described unusual and sometimes aggressive behavior, and were often accompanied by amnesia for the events. Advise patients to reduce the amount of alcohol they consume while taking CHANTIX until they know whether CHANTIX affects their tolerance for alcohol [see Adverse Reactions (6.2)].

5.4 Accidental Injury

There have been postmarketing reports of traffic accidents, near-miss incidents in traffic, or other accidental injuries in patients taking CHANTIX. In some cases, the patients reported somnolence, dizziness, loss of consciousness or difficulty concentrating that resulted in impairment, or concern about potential impairment, in driving or operating machinery. Advise patients to use caution driving or operating machinery or engaging in other potentially hazardous activities until they know how CHANTIX may affect them.

5.5 Cardiovascular Events

A comprehensive evaluation of cardiovascular (CV) risk with CHANTIX suggests that patients with underlying CV disease may be at increased risk; however, these concerns must be balanced with the health benefits of smoking cessation. CV risk has been assessed for CHANTIX in randomized controlled trials (RCT) and meta-analyses of RCTs. In a smoking cessation trial in patients with stable CV disease, CV events were infrequent overall; however, nonfatal myocardial infarction (MI) and nonfatal stroke occurred more frequently in patients treated with CHANTIX compared to placebo. All-cause and CV mortality was lower in patients treated with CHANTIX [see Clinical Studies (14.8)]. This study was included in a meta-analysis of 15 CHANTIX efficacy trials in various clinical populations that showed an increased hazard ratio for Major Adverse Cardiovascular Events (MACE) of 1.95; however, the finding was not statistically significant (95% CI: 0.79, 4.82). In the large postmarketing neuropsychiatric safety outcome trial, an analysis of adjudicated MACE events was conducted for patients while in the trial and during a 28-week non-treatment extension period. Few MACE events occurred during the trial; therefore, the findings did not contribute substantively to the understanding of CV risk with CHANTIX. Instruct patients to notify their healthcare providers of new or worsening CV symptoms and to seek immediate medical attention if they experience signs and symptoms of MI or stroke [see Clinical Studies (14.10)].

5.6 Somnambulism

Cases of somnambulism have been reported in patients taking CHANTIX. Some cases described harmful behavior to self, others, or property. Instruct patients to discontinue CHANTIX and notify their healthcare provider if they experience somnambulism [see Adverse Reactions (6.2)].

5.7 Angioedema and Hypersensitivity Reactions

There have been postmarketing reports of hypersensitivity reactions including angioedema in patients treated with CHANTIX [see Adverse Reactions (6.2), Patient Counseling Information (17)]. Clinical signs included swelling of the face, mouth (tongue, lips, and gums), extremities, and neck (throat and larynx). There were infrequent reports of life-threatening angioedema requiring emergent medical attention due to respiratory compromise. Instruct patients to discontinue CHANTIX and immediately seek medical care if they experience these symptoms.

5.8 Serious Skin Reactions

There have been postmarketing reports of rare but serious skin reactions, including Stevens-Johnson Syndrome and erythema multiforme, in patients using CHANTIX [see Adverse Reactions (6.2)]. As these skin reactions can be life-threatening, instruct patients to stop taking CHANTIX and contact a healthcare provider immediately at the first appearance of a skin rash with mucosal lesions or any other signs of hypersensitivity.

5.9 Nausea

Nausea was the most common adverse reaction reported with CHANTIX treatment. Nausea was generally described as mild or moderate and often transient; however, for some patients, it was persistent over several months. The incidence of nausea was dose-dependent. Initial dose-titration was beneficial in reducing the occurrence of nausea. For patients treated to the maximum recommended dose of 1 mg twice daily following initial dosage titration, the incidence of nausea was 30% compared with 10% in patients taking a comparable placebo regimen. In patients taking CHANTIX 0.5 mg twice daily following initial titration, the incidence was 16% compared with 11% for placebo. Approximately 3% of patients treated with CHANTIX 1 mg twice daily in studies involving 12 weeks of treatment discontinued treatment prematurely because of nausea. For patients with intolerable nausea, a dose reduction should be considered.

6 ADVERSE REACTIONS

The following serious adverse reactions were reported in postmarketing experience and are discussed in greater detail in other sections of the labeling:

- Neuropsychiatric Adverse Events including Suicidality [see Warnings and Precautions (5.1)]
- Seizures [see Warnings and Precautions (5.2)]
- Interaction with Alcohol [see Warnings and Precautions (5.3)]
- Accidental Injury [see Warnings and Precautions (5.4)]
- Cardiovascular Events [see Warnings and Precautions (5.5)]
- Somnambulism [see Warnings and Precautions (5.6)]
- Angioedema and Hypersensitivity Reactions [see Warnings and Precautions (5.7)]
- Serious Skin Reactions [see Warnings and Precautions (5.8)]

In the placebo-controlled premarketing studies, the most common adverse events associated with CHANTIX (>5% and twice the rate seen in placebo-treated patients) were nausea, abnormal (vivid, unusual, or strange) dreams, constipation, flatulence, and vomiting.

The treatment discontinuation rate due to adverse events in patients dosed with 1 mg twice daily was 12% for CHANTIX, compared to 10% for placebo in studies of three months' treatment. In this group, the discontinuation rates that are higher than placebo for the most common adverse events in CHANTIX-treated patients were as follows: nausea (3% vs. 0.5% for placebo), insomnia (1.2% vs. 1.1% for placebo), and abnormal dreams (0.3% vs. 0.2% for placebo).

Smoking cessation, with or without treatment, is associated with nicotine withdrawal symptoms and has also been associated with the exacerbation of underlying psychiatric illness.

6.1 Clinical Trials Experience

Because clinical trials are conducted under widely varying conditions, the adverse reactions rates observed in the clinical studies of a drug cannot be directly compared to rates in the clinical trials of another drug and may not reflect the rates observed in clinical practice.

During the premarketing development of CHANTIX, over 4500 subjects were exposed to CHANTIX, with over 450 treated for at least 24 weeks and approximately 100 for a year. Most study participants were treated for 12 weeks or less.

The most common adverse event associated with CHANTIX treatment is nausea, occurring in 30% of patients treated at the recommended dose, compared with 10% in patients taking a comparable placebo regimen [see Warnings and Precautions (5.9)].

Table 1 shows the adverse events for CHANTIX and placebo in the 12- week fixed dose premarketing studies with titration in the first week [Studies 2 (titrated arm only), 4, and 5]. Adverse events were categorized using the Medical Dictionary for Regulatory Activities (MedDRA, Version 7.1).

MedDRA High Level Group Terms (HLGT) reported in ≥5% of patients in the CHANTIX 1 mg twice daily dose group, and more commonly than in the placebo group, are listed, along with subordinate Preferred Terms (PT) reported in ≥1% of CHANTIX patients (and at least 0.5% more frequent than placebo). Closely related Preferred Terms such as 'Insomnia', 'Initial insomnia', 'Middle insomnia', 'Early morning awakening' were grouped, but individual patients reporting two or more grouped events are only counted once.

Table 1. Common Treatment Emergent AEs (%) in the Fixed-Dose, Placebo-Controlled Studies (HLGTs ≥5% of Patients in the 1 mg BID CHANTIX Group and More Commonly than Placebo and PT ≥1% in the 1 mg BID CHANTIX Group, and 1 mg BID CHANTIX at Least 0.5% More than Placebo)
SYSTEM ORGAN CLASS High Level Group Term | CHANTIX 0.5 mg BID | CHANTIX 1 mg BID | Placebo
Preferred Term | N=129 | N=821 | N=805
GASTROINTESTINAL (GI)
GI Signs and Symptoms
Nausea | 16 | 30 | 10
Abdominal Pain [Includes PTs Abdominal (pain, pain upper, pain lower, discomfort, tenderness, distension) and Stomach discomfort] | 5 | 7 | 5
Flatulence | 9 | 6 | 3
Dyspepsia | 5 | 5 | 3
Vomiting | 1 | 5 | 2
GI Motility/Defecation Conditions
Constipation | 5 | 8 | 3
Gastroesophageal reflux disease | 1 | 1 | 0
Salivary Gland Conditions
Dry mouth | 4 | 6 | 4
PSYCHIATRIC DISORDERS
Sleep Disorder/Disturbances
Insomnia [Includes PTs Insomnia/Initial insomnia/Middle insomnia/Early morning awakening] | 19 | 18 | 13
Abnormal dreams | 9 | 13 | 5
Sleep disorder | 2 | 5 | 3
Nightmare | 2 | 1 | 0
NERVOUS SYSTEM
Headaches
Headache | 19 | 15 | 13
Neurological Disorders NEC
Dysgeusia | 8 | 5 | 4
Somnolence | 3 | 3 | 2
Lethargy | 2 | 1 | 0
GENERAL DISORDERS
General Disorders NEC
Fatigue/Malaise/Asthenia | 4 | 7 | 6
RESPIR/THORACIC/MEDIAST
Respiratory Disorders NEC
Rhinorrhea | 0 | 1 | 0
Dyspnea | 2 | 1 | 1
Upper Respiratory Tract Disorder | 7 | 5 | 4
SKIN/SUBCUTANEOUS TISSUE
Epidermal and Dermal Conditions
Rash | 1 | 3 | 2
Pruritis | 0 | 1 | 1
METABOLISM and NUTRITION
Appetite/General Nutrition Disorders
Increased appetite | 4 | 3 | 2
Decreased appetite/Anorexia | 1 | 2 | 1

The overall pattern and frequency of adverse events during the longer-term premarketing trials was similar to those described in Table 1, though several of the most common events were reported by a greater proportion of patients with long-term use (e.g., nausea was reported in 40% of patients treated with CHANTIX 1 mg twice daily in a one year study, compared to 8% of placebo-treated patients).

Following is a list of treatment-emergent adverse events reported by patients treated with CHANTIX during all premarketing clinical trials and updated based on pooled data from 18 placebo-controlled pre- and postmarketing studies, including approximately 5,000 patients treated with varenicline. Adverse events were categorized using MedDRA, Version 16.0. The listing does not include those events already listed in the previous tables or elsewhere in labeling, those events for which a drug cause was remote, those events which were so general as to be uninformative, and those events reported only once which did not have a substantial probability of being acutely life-threatening.

Blood and Lymphatic System Disorders. Infrequent: anemia, lymphadenopathy. Rare: leukocytosis, splenomegaly, thrombocytopenia.

Cardiac Disorders. Infrequent: angina pectoris, myocardial infarction, palpitations, tachycardia. Rare: acute coronary syndrome, arrhythmia, atrial fibrillation, bradycardia, cardiac flutter, cor pulmonale, coronary artery disease, ventricular extrasystoles.

Ear and Labyrinth Disorders. Infrequent: tinnitus, vertigo. Rare: deafness, Meniere's disease.

Endocrine Disorders. Infrequent: thyroid gland disorders.

Eye Disorders. Infrequent: conjunctivitis, eye irritation, eye pain, vision blurred, visual impairment. Rare: blindness transient, cataract subcapsular, dry eye, night blindness, ocular vascular disorder, photophobia, vitreous floaters.

Gastrointestinal Disorders. Frequent: diarrhea, toothache. Infrequent: dysphagia, eructation, gastritis, gastrointestinal hemorrhage, mouth ulceration. Rare: enterocolitis, esophagitis, gastric ulcer, intestinal obstruction, pancreatitis acute.

General Disorders and Administration Site Conditions. Frequent: chest pain. Infrequent: chest discomfort, chills, edema, influenza-like illness, pyrexia.

Hepatobiliary Disorders. Rare: gall bladder disorder.

Investigations. Frequent: liver function test abnormal, weight increased. Infrequent: electrocardiogram abnormal. Rare: muscle enzyme increased, urine analysis abnormal.

Metabolism and Nutrition Disorders. Infrequent: diabetes mellitus, hypoglycemia. Rare: hyperlipidemia, hypokalemia.

Musculoskeletal and Connective Tissue Disorders. Frequent: arthralgia, back pain, myalgia. Infrequent: arthritis, muscle cramp, musculoskeletal pain. Rare: myositis, osteoporosis.

Nervous System Disorders. Frequent: disturbance in attention, dizziness. Infrequent: amnesia, convulsion, migraine, parosmia, syncope, tremor. Rare: balance disorder, cerebrovascular accident, dysarthria, mental impairment, multiple sclerosis, VIIth nerve paralysis, nystagmus, psychomotor hyperactivity, psychomotor skills impaired, restless legs syndrome, sensory disturbance, transient ischemic attack, visual field defect.

Psychiatric Disorders. Infrequent: dissociation, libido decreased, mood swings, thinking abnormal. Rare: bradyphrenia, disorientation, euphoric mood.

Renal and Urinary Disorders. Infrequent: nocturia, pollakiuria, urine abnormality. Rare: nephrolithiasis, polyuria, renal failure acute, urethral syndrome, urinary retention.

Reproductive System and Breast Disorders. Frequent: menstrual disorder. Infrequent: erectile dysfunction. Rare: sexual dysfunction.

Respiratory, Thoracic and Mediastinal Disorders. Frequent: respiratory disorders. Infrequent: asthma, epistaxis, rhinitis allergic, upper respiratory tract inflammation. Rare: pleurisy, pulmonary embolism.

Skin and Subcutaneous Tissue Disorders. Infrequent: acne, dry skin, eczema, erythema, hyperhidrosis, urticaria. Rare: photosensitivity reaction, psoriasis.

Vascular Disorders. Infrequent: hot flush. Rare: thrombosis.

CHANTIX has also been studied in postmarketing trials including (1) a trial conducted in patients with chronic obstructive pulmonary disease (COPD), (2) a trial conducted in generally healthy patients (similar to those in the premarketing studies) in which they were allowed to select a quit date between days 8 and 35 of treatment ("alternative quit date instruction trial"), (3) a trial conducted in patients who did not succeed in stopping smoking during prior CHANTIX therapy, or who relapsed after treatment ("re-treatment trial"), (4) a trial conducted in patients with stable cardiovascular disease, (5) a trial conducted in patients with stable schizophrenia or schizoaffective disorder, (6) a trial conducted in patients with major depressive disorder, (7) a postmarketing neuropsychiatric safety outcome trial in patients without or with a history of psychiatric disorder, (8) a non-treatment extension of the postmarketing neuropsychiatric safety outcome trial that assessed CV safety, (9) a trial in patients who were not able or willing to quit abruptly and who were instructed to quit gradually ("gradual approach to quitting smoking trial").

Adverse events in the trial of patients with COPD (1), in the alternative quit date instruction trial (2), and in the gradual approach to quitting smoking trial (9) were similar to those observed in premarketing studies. In the re-treatment trial (3), the profile of common adverse events was similar to that previously reported, but, in addition, varenicline-treated patients also commonly reported diarrhea (6% vs. 4% in placebo-treated patients), depressed mood disorders and disturbances (6% vs. 1%), and other mood disorders and disturbances (5% vs. 2%).

In the trial of patients with stable cardiovascular disease (4), more types and a greater number of cardiovascular events were reported compared to premarketing studies, as shown in Table 1 and in Table 2 below.

Table 2. Cardiovascular Mortality and Nonfatal Cardiovascular Events (%) with a Frequency >1% in Either Treatment Group in the Trial of Patients with Stable Cardiovascular Disease
 | CHANTIX 1 mg BID | Placebo
 | N=353 | N=350
Adverse Events ≥1% in either treatment group
Up to 30 days after treatment
Angina pectoris | 3.7 | 2.0
Chest pain | 2.5 | 2.3
Peripheral edema | 2.0 | 1.1
Hypertension | 1.4 | 2.6
Palpitations | 0.6 | 1.1
Adjudicated Cardiovascular Mortality (up to 52 weeks) | 0.3 | 0.6
Adjudicated Nonfatal Serious Cardiovascular Events ≥1% in either treatment group
Up to 30 days after treatment
Nonfatal MI | 1.1 | 0.3
Hospitalization for angina pectoris | 0.6 | 1.1
Beyond 30 days after treatment and up to 52 weeks
Need for coronary revascularization [some procedures were part of management of nonfatal MI and hospitalization for angina] | 2.0 | 0.6
Hospitalization for angina pectoris | 1.7 | 1.1
New diagnosis of peripheral vascular disease (PVD) or admission for a PVD procedure | 1.4 | 0.6

In the trial of patients with stable schizophrenia or schizoaffective disorder (5), 128 smokers on antipsychotic medication were randomized 2:1 to varenicline (1 mg twice daily) or placebo for 12 weeks with 12-week non-drug follow-up. The most common treatment emergent adverse events reported in this trial are shown in Table 3 below.

Table 3. Common Treatment Emergent AEs (%) in the Trial of Patients with Stable Schizophrenia or Schizoaffective Disorder
 | CHANTIX 1 mg BID | Placebo
 | N=84 | N=43
Adverse Events ≥10% in the varenicline group
Nausea | 24 | 14
Headache | 11 | 19
Vomiting | 11 | 9
Psychiatric Adverse Events ≥5% and at a higher rate than in the placebo group
Insomnia | 10 | 5

For the trial of patients with major depressive disorder (6), the most common treatment emergent adverse events reported are shown in Table 4 below. Additionally, in this trial, patients treated with varenicline were more likely than patients treated with placebo to report one of events related to hostility and aggression (3% vs. 1%).

Table 4. Common Treatment Emergent AEs (%) in the Trial of Patients with Major Depressive Disorder
 | CHANTIX 1 mg BID | Placebo
 | N=256 | N=269
Adverse Events ≥10% in either treatment group
Nausea | 27 | 10
Headache | 17 | 11
Abnormal dreams | 11 | 8
Insomnia | 11 | 5
Irritability | 11 | 8
Psychiatric Adverse Events ≥2% in any treatment group and not included above
Depressed mood disorders and disturbances | 11 | 9
Anxiety | 7 | 9
Agitation | 7 | 4
Tension | 4 | 3
Hostility | 2 | 0.4
Restlessness | 2 | 2

In the trial of patients without or with a history of psychiatric disorder (7), the most common adverse events in subjects treated with varenicline were similar to those observed in premarketing studies. Most common treatment-emergent adverse events reported in this trial are shown in Table 5 below.

Table 5. Treatment Emergent Common AEs (%) in the Trial of Patients without or with a History of Psychiatric Disorder
 | CHANTIX 1 mg BID | Placebo
Adverse Events ≥10% in the varenicline group
Entire study population, N | 1982 | 1979
Nausea | 25 | 7
Headache | 12 | 10
Psychiatric Adverse Events ≥2% in any treatment group
Non-psychiatric cohort, N | 975 | 982
Abnormal dreams | 8 | 4
Agitation | 3 | 3
Anxiety | 5 | 6
Depressed mood | 3 | 3
Insomnia | 10 | 7
Irritability | 3 | 4
Sleep disorder | 3 | 2
Psychiatric cohort, N | 1007 | 997
Abnormal dreams | 12 | 5
Agitation | 5 | 4
Anxiety | 8 | 6
Depressed mood | 5 | 5
Depression | 5 | 5
Insomnia | 9 | 7
Irritability | 5 | 7
Nervousness | 2 | 3
Sleep disorder | 3 | 2

In the non-treatment extension of the postmarketing neuropsychiatric safety outcomes trial that assessed CV safety (8), the most common adverse events in subjects treated with varenicline and occurring up to 30 days after last dose of treatment were similar to those observed in premarketing studies.

6.2 Postmarketing Experience

The following adverse events have been reported during post-approval use of CHANTIX. Because these events are reported voluntarily from a population of uncertain size, it is not possible to reliably estimate their frequency or establish a causal relationship to drug exposure.

There have been reports of depression, mania, psychosis, hallucinations, paranoia, delusions, homicidal ideation, aggression, hostility, anxiety, and panic, as well as suicidal ideation, suicide attempt, and completed suicide in patients attempting to quit smoking while taking CHANTIX [see Warnings and Precautions (5.1)].

There have been postmarketing reports of new or worsening seizures in patients treated with CHANTIX [see Warnings and Precautions (5.2)].

There have been postmarketing reports of patients experiencing increased intoxicating effects of alcohol while taking CHANTIX. Some reported neuropsychiatric events, including unusual and sometimes aggressive behavior [see Warnings and Precautions (5.1) and (5.3)].

There have been reports of hypersensitivity reactions, including angioedema [see Warnings and Precautions (5.7)].

There have also been reports of serious skin reactions, including Stevens-Johnson Syndrome and erythema multiforme, in patients taking CHANTIX [see Warnings and Precautions (5.8)].

There have been reports of myocardial infarction (MI) and cerebrovascular accident (CVA) including ischemic and hemorrhagic events in patients taking CHANTIX. In the majority of the reported cases, patients had pre-existing cardiovascular disease and/or other risk factors. Although smoking is a risk factor for MI and CVA, based on temporal relationship between medication use and events, a contributory role of varenicline cannot be ruled out [see Warnings and Precautions (5.5)].

There have been reports of hyperglycemia in patients following initiation of CHANTIX.

There have been reports of somnambulism, some resulting in harmful behavior to self, others, or property in patients treated with CHANTIX [see Warnings and Precautions (5.6)].

7 DRUG INTERACTIONS

Based on varenicline characteristics and clinical experience to date, CHANTIX has no clinically meaningful pharmacokinetic drug interactions [see Clinical Pharmacology (12.3)].

7.1 Use with Other Drugs for Smoking Cessation

Safety and efficacy of CHANTIX in combination with other smoking cessation therapies have not been studied.

Bupropion

Varenicline (1 mg twice daily) did not alter the steady-state pharmacokinetics of bupropion (150 mg twice daily) in 46 smokers. The safety of the combination of bupropion and varenicline has not been established.

Nicotine replacement therapy (NRT)

Although co-administration of varenicline (1 mg twice daily) and transdermal nicotine (21 mg/day) for up to 12 days did not affect nicotine pharmacokinetics, the incidence of nausea, headache, vomiting, dizziness, dyspepsia, and fatigue was greater for the combination than for NRT alone. In this study, eight of twenty-two (36%) patients treated with the combination of varenicline and NRT prematurely discontinued treatment due to adverse events, compared to 1 of 17 (6%) of patients treated with NRT and placebo.

7.2 Effect of Smoking Cessation on Other Drugs

Physiological changes resulting from smoking cessation, with or without treatment with CHANTIX, may alter the pharmacokinetics or pharmacodynamics of certain drugs (e.g., theophylline, warfarin, insulin) for which dosage adjustment may be necessary.

8 USE IN SPECIFIC POPULATIONS

8.1 Pregnancy

Risk Summary

Available data have not suggested an increased risk for major birth defects following exposure to varenicline in pregnancy, compared with women who smoke [see Data]. Smoking during pregnancy is associated with maternal, fetal, and neonatal risks (see Clinical Considerations). In animal studies, varenicline did not result in major malformations but caused decreased fetal weights in rabbits when dosed during organogenesis at exposures equivalent to 50 times the exposure at the maximum recommended human dose (MRHD). Additionally, administration of varenicline to pregnant rats during organogenesis through lactation produced developmental toxicity in offspring at maternal exposures equivalent to 36 times human exposure at the MRHD [see Data].

The estimated background risk of oral clefts is increased by approximately 30% in infants of women who smoke during pregnancy, compared to pregnant women who do not smoke. The background risk of other major birth defects and miscarriage for the indicated population are unknown. In the US general population, the estimated background risk of major birth defects and miscarriage in clinically recognized pregnancies is 2–4% and 15–20%, respectively.

Clinical Considerations

Disease-Associated Maternal and/or Embryo/Fetal Risk

Smoking during pregnancy causes increased risks of orofacial clefts, premature rupture of membranes, placenta previa, placental abruption, ectopic pregnancy, fetal growth restriction and low birth weight, stillbirth, preterm delivery and shortened gestation, neonatal death, sudden infant death syndrome and reduction of lung function in infants. It is not known whether quitting smoking with CHANTIX during pregnancy reduces these risks.

Data

Human Data

A population-based observational cohort study using the national registers of Denmark and Sweden compared pregnancy and birth outcomes among women exposed to varenicline (N=335, includes 317 first trimester exposed) with women who smoked during pregnancy (N=78,412) and with non-smoking pregnant women (N=806,438). The prevalence of major malformations, the primary outcome, was similar in all groups, including between smoking and non-smoking groups. The prevalence of adverse perinatal outcomes in the varenicline-exposed cohort was not greater than in the cohort of women who smoked, and differed somewhat between the three cohorts. The prevalences of the primary and secondary outcomes are shown in Table 6.

Table 6. Summary of Primary and Secondary Outcomes for Three Birth Cohorts
Outcome | Varenicline Cohort (n=335) | Smoking Cohort (n=78,412) | Non-Smoking Cohort (n=806,438)
Major congenital malformation [Included only live births in the cohorts. Prevalence among first trimester varenicline-exposed pregnancies (11/317 [3.5%]).] | 12 / 334 (3.6%) | 3,382 / 78,028 (4.3%) | 33,950 /804,020 (4.2%)
Stillbirth | 1 (0.3%) | 384 (0.5%) | 2,418 (0.3%)
Small for gestational age | 42 (12.5%) | 13,433 (17.1%) | 73,135 (9.1%)
Preterm birth | 25 (7.5%) | 6,173 (7.9%) | 46,732 (5.8%)
Premature rupture of membranes | 12 (3.6%) | 4,246 (5.4%) | 30,641 (3.8%)
Sudden infant death syndrome [There was a lag in death data in Denmark, so the cohorts were smaller.] | 0/307 (0.0%) | 51/71,720 (0.1%) | 58/755,939 (<0.1%)

The study limitations include the inability to capture malformations in pregnancies that do not result in a live birth, and possible misclassification of outcome and of exposure to varenicline or to smoking.

Other small epidemiological studies of pregnant women exposed to varenicline did not identify an association with major malformations, consistent with the Danish and Swedish observational cohort study. Methodological limitations of these studies include small samples and lack of adequate controls.

Overall, available studies cannot definitely establish or exclude any varenicline-associated risk during pregnancy.

Animal Data

Pregnant rats and rabbits received varenicline succinate during organogenesis at oral doses up to 15 and 30 mg/kg/day, respectively. While no fetal structural abnormalities occurred in either species, maternal toxicity, characterized by reduced body weight gain, and reduced fetal weights occurred in rabbits at the highest dose (exposures 50 times the human exposure at the MRHD of 1 mg twice daily based on AUC). Fetal weight reduction did not occur in rabbits at exposures 23 times the human exposure at the MRHD based on AUC.

In a pre- and postnatal development study, pregnant rats received up to 15 mg/kg/day of oral varenicline succinate from organogenesis through lactation. Maternal toxicity, characterized by a decrease in body weight gain was observed at 15 mg/kg/day (36 times the human exposure at the MRHD based on AUC). However, decreased fertility and increased auditory startle response occurred in offspring at the highest maternal dose of 15 mg/kg/day.

8.2 Lactation

Risk Summary

There are no data on the presence of varenicline in human milk, the effects on the breastfed infant, or the effects on milk production. In animal studies varenicline was present in milk of lactating rats [see Data]. However, due to species-specific differences in lactation physiology, animal data may not reliably predict drug levels in human milk. The lack of clinical data during lactation precludes a clear determination of the risk of CHANTIX to an infant during lactation; however the developmental and health benefits of breastfeeding should be considered along with the mother's clinical need for CHANTIX and any potential adverse effects on the breastfed child from CHANTIX or from the underlying maternal condition.

Clinical Considerations

Because there are no data on the presence of varenicline in human milk and the effects on the breastfed infant, breastfeeding women should monitor their infant for seizures and excessive vomiting, which are adverse reactions that have occurred in adults that may be clinically relevant in breastfeeding infants.

Data

In a pre- and postnatal development study, pregnant rats received up to 15 mg/kg/day of oral varenicline succinate through gestation and lactation Mean serum concentrations of varenicline in the nursing pups were 5–22% of maternal serum concentrations.

8.4 Pediatric Use

CHANTIX is not recommended for use in pediatric patients 16 years of age or younger because its efficacy in this population was not demonstrated.

Single and multiple-dose pharmacokinetics of varenicline have been investigated in pediatric patients aged 12 to 17 years old (inclusive) and were approximately dose-proportional over the 0.5 mg to 2 mg daily dose range studied. Steady-state systemic exposure in adolescent patients of bodyweight >55 kg, as assessed by AUC (0-24), was comparable to that noted for the same doses in the adult population. When 0.5 mg BID was given, steady-state daily exposure of varenicline was, on average, higher (by approximately 40%) in adolescent patients with bodyweight ≤55 kg compared to that noted in the adult population.

The efficacy and safety of varenicline was evaluated in a randomized, double-blind, placebo-controlled study of 312 patients aged 12 to 19 years, who smoked an average of at least 5 cigarettes per day during the 30 days prior to recruitment, had a score of at least 4 on the Fagerstrom Test for Nicotine Dependence scale, and at least one previous failed quit attempt. Patients were stratified by age (12 to 16 years of age, n=216 and 17 to 19 years of age, n=96) and by body weight (≤55 kg and >55 kg). Patients were randomized to one of two doses of varenicline, adjusted by weight to provide plasma levels in the efficacious range (based on adult studies) and placebo. Patients received treatment for 12 weeks, followed by a non-treatment period of 40 weeks, along with age-appropriate counseling throughout the study. Results from this study showed that varenicline, at either dose studied, did not improve continuous abstinence rates at weeks 9 through 12 of treatment compared with placebo in subjects 12 to 19 years of age. The varenicline safety profile in this study was consistent with that observed in adult studies.

8.5 Geriatric Use

A combined single- and multiple-dose pharmacokinetic study demonstrated that the pharmacokinetics of 1 mg varenicline given once daily or twice daily to 16 healthy elderly male and female smokers (aged 65–75 years) for 7 consecutive days was similar to that of younger subjects. No overall differences in safety or effectiveness were observed between these subjects and younger subjects, and other reported clinical experience has not identified differences in responses between the elderly and younger patients, but greater sensitivity of some older individuals cannot be ruled out.

Varenicline is known to be substantially excreted by the kidney, and the risk of toxic reactions to this drug may be greater in patients with impaired renal function. Because elderly patients are more likely to have decreased renal function, care should be taken in dose selection, and it may be useful to monitor renal function [see Dosage and Administration (2.2)].

No dosage adjustment is recommended for elderly patients.

8.6 Renal Impairment

Varenicline is substantially eliminated by renal glomerular filtration along with active tubular secretion. Dose reduction is not required in patients with mild-to-moderate renal impairment. For patients with severe renal impairment (estimated creatinine clearance <30 mL/min), and for patients with end-stage renal disease undergoing hemodialysis, dosage adjustment is needed [see Dosage and Administration (2.2), Clinical Pharmacology (12.3)].

9 DRUG ABUSE AND DEPENDENCE

9.1 Controlled Substance

Varenicline is not a controlled substance.

9.3 Dependence

Humans

Fewer than 1 out of 1,000 patients reported euphoria in clinical trials with CHANTIX. At higher doses (greater than 2 mg), CHANTIX produced more frequent reports of gastrointestinal disturbances such as nausea and vomiting. There is no evidence of dose-escalation to maintain therapeutic effects in clinical studies, which suggests that tolerance does not develop. Abrupt discontinuation of CHANTIX was associated with an increase in irritability and sleep disturbances in up to 3% of patients. This suggests that, in some patients, varenicline may produce mild physical dependence which is not associated with addiction.

In a human laboratory abuse liability study, a single oral dose of 1 mg varenicline did not produce any significant positive or negative subjective responses in smokers. In non-smokers, 1 mg varenicline produced an increase in some positive subjective effects, but this was accompanied by an increase in negative adverse effects, especially nausea. A single oral dose of 3 mg varenicline uniformly produced unpleasant subjective responses in both smokers and non-smokers.

Animals

Studies in rodents have shown that varenicline produces behavioral responses similar to those produced by nicotine. In rats trained to discriminate nicotine from saline, varenicline produced full generalization to the nicotine cue. In self-administration studies, the degree to which varenicline substitutes for nicotine is dependent upon the requirement of the task. Rats trained to self-administer nicotine under easy conditions continued to self-administer varenicline to a degree comparable to that of nicotine; however in a more demanding task, rats self-administered varenicline to a lesser extent than nicotine. Varenicline pretreatment also reduced nicotine self-administration.

10 OVERDOSAGE

In case of overdose, standard supportive measures should be instituted as required.

Varenicline has been shown to be dialyzed in patients with end-stage renal disease [see Clinical Pharmacology (12.3)], however, there is no experience in dialysis following overdose.

11 DESCRIPTION

CHANTIX tablets contain varenicline (as the tartrate salt), which is a partial nicotinic agonist selective for α4β2 nicotinic acetylcholine receptor subtypes.

Varenicline, as the tartrate salt, is a powder which is a white to off-white to slightly yellow solid with the following chemical name: 7,8,9,10-tetrahydro-6,10-methano-6H-pyrazino[2,3- h][3]benzazepine, (2R,3R)-2,3-dihydroxybutanedioate (1:1). It is highly soluble in water. Varenicline tartrate has a molecular weight of 361.35 Daltons, and a molecular formula of C13H13N3 ∙ C4H6O6. The chemical structure is:

CHANTIX is supplied for oral administration in two strengths: a 0.5 mg capsular biconvex, white to off-white, film-coated tablet debossed with "Pfizer" on one side and "CHX 0.5" on the other side and a 1 mg capsular biconvex, light blue film-coated tablet debossed with "Pfizer" on one side and "CHX 1.0" on the other side. Each 0.5 mg CHANTIX tablet contains 0.85 mg of varenicline tartrate equivalent to 0.5 mg of varenicline free base; each 1 mg CHANTIX tablet contains 1.71 mg of varenicline tartrate equivalent to 1 mg of varenicline free base. The following inactive ingredients are included in the tablets: microcrystalline cellulose, anhydrous dibasic calcium phosphate, croscarmellose sodium, colloidal silicon dioxide, magnesium stearate, Opadry® White (for 0.5 mg), Opadry® Blue (for 1 mg), and Opadry® Clear.

12 CLINICAL PHARMACOLOGY

12.1 Mechanism of Action

Varenicline binds with high affinity and selectivity at α4β2 neuronal nicotinic acetylcholine receptors. The efficacy of CHANTIX in smoking cessation is believed to be the result of varenicline's activity at α4β2 sub-type of the nicotinic receptor where its binding produces agonist activity, while simultaneously preventing nicotine binding to these receptors.

Electrophysiology studies in vitro and neurochemical studies in vivo have shown that varenicline binds to α4β2 neuronal nicotinic acetylcholine receptors and stimulates receptor-mediated activity, but at a significantly lower level than nicotine. Varenicline blocks the ability of nicotine to activate α4β2 receptors and thus to stimulate the central nervous mesolimbic dopamine system, believed to be the neuronal mechanism underlying reinforcement and reward experienced upon smoking. Varenicline is highly selective and binds more potently to α4β2 receptors than to other common nicotinic receptors (>500-fold α3β4, >3,500-fold α7, >20,000-fold α1βγδ), or to non-nicotinic receptors and transporters (>2,000-fold). Varenicline also binds with moderate affinity (Ki = 350 nM) to the 5-HT3 receptor.

12.3 Pharmacokinetics

Absorption

Maximum plasma concentrations of varenicline occur typically within 3–4 hours after oral administration. Following administration of multiple oral doses of varenicline, steady-state conditions were reached within 4 days. Over the recommended dosing range, varenicline exhibits linear pharmacokinetics after single or repeated doses.

In a mass balance study, absorption of varenicline was virtually complete after oral administration and systemic availability was ~90%.

Food Effect

Oral bioavailability of varenicline is unaffected by food or time-of-day dosing.

Distribution

Plasma protein binding of varenicline is low (≤20%) and independent of both age and renal function.

Elimination

The elimination half-life of varenicline is approximately 24 hours.

Metabolism

Varenicline undergoes minimal metabolism, with 92% excreted unchanged in the urine.

Excretion

Renal elimination of varenicline is primarily through glomerular filtration along with active tubular secretion possibly via the organic cation transporter, OCT2.

Specific Populations

There are no clinically meaningful differences in varenicline pharmacokinetics due to age, race, gender, smoking status, or use of concomitant medications, as demonstrated in specific pharmacokinetic studies and in population pharmacokinetic analyses.

Age: Geriatric Patients

A combined single- and multiple-dose pharmacokinetic study demonstrated that the pharmacokinetics of 1 mg varenicline given once daily or twice daily to 16 healthy elderly male and female smokers (aged 65–75 years) for 7 consecutive days was similar to that of younger subjects.

Age: Pediatric Patients

CHANTIX is not recommended for use in pediatric patients 16 years of age or younger because its efficacy in this population was not demonstrated [see Use in Specific Populations (8.4)].

Renal Impairment

Varenicline pharmacokinetics were unchanged in subjects with mild renal impairment (estimated creatinine clearance >50 mL/min and ≤80 mL/min). In subjects with moderate renal impairment (estimated creatinine clearance ≥30 mL/min and ≤50 mL/min), varenicline exposure increased 1.5-fold compared with subjects with normal renal function (estimated creatinine clearance >80 mL/min). In subjects with severe renal impairment (estimated creatinine clearance <30 mL/min), varenicline exposure was increased 2.1-fold. In subjects with end-stage-renal disease (ESRD) undergoing a three-hour session of hemodialysis for three days a week, varenicline exposure was increased 2.7-fold following 0.5 mg once daily administration for 12 days. The plasma Cmax and AUC of varenicline noted in this setting were similar to those of healthy subjects receiving 1 mg twice daily [see Dosage and Administration (2.2), Use in Specific Populations (8.6)]. Additionally, in subjects with ESRD, varenicline was efficiently removed by hemodialysis [see Overdosage (10)].

Hepatic Impairment

Due to the absence of significant hepatic metabolism, varenicline pharmacokinetics should be unaffected in patients with hepatic impairment.

Drug-Drug Interactions

In vitro studies demonstrated that varenicline does not inhibit the following cytochrome P450 enzymes (IC50 >6400 ng/mL): 1A2, 2A6, 2B6, 2C8, 2C9, 2C19, 2D6, 2E1, and 3A4/5. Also, in human hepatocytes in vitro, varenicline does not induce the cytochrome P450 enzymes 1A2 and 3A4.

In vitro studies demonstrated that varenicline does not inhibit human renal transport proteins at therapeutic concentrations. Therefore, drugs that are cleared by renal secretion (e.g., metformin [see below]) are unlikely to be affected by varenicline.

In vitro studies demonstrated the active renal secretion of varenicline is mediated by the human organic cation transporter OCT2. Co-administration with inhibitors of OCT2 (e.g., cimeditine [see below]) may not necessitate a dose adjustment of CHANTIX as the increase in systemic exposure to CHANTIX is not expected to be clinically meaningful. Furthermore, since metabolism of varenicline represents less than 10% of its clearance, drugs known to affect the cytochrome P450 system are unlikely to alter the pharmacokinetics of CHANTIX [see Clinical Pharmacology (12.3)]; therefore, a dose adjustment of CHANTIX would not be required.

Drug interaction studies were performed with varenicline and digoxin, warfarin, transdermal nicotine, bupropion, cimetidine, and metformin. No clinically meaningful pharmacokinetic drug-drug interactions have been identified.

Metformin

When co-administered to 30 smokers, varenicline (1 mg twice daily) did not alter the steady-state pharmacokinetics of metformin (500 mg twice daily), which is a substrate of OCT2. Metformin had no effect on varenicline steady-state pharmacokinetics.

Cimetidine

Co-administration of an OCT2 inhibitor, cimetidine (300 mg four times daily), with varenicline (2 mg single dose) to 12 smokers increased the systemic exposure of varenicline by 29% (90% CI: 21.5%, 36.9%) due to a reduction in varenicline renal clearance.

Digoxin

Varenicline (1 mg twice daily) did not alter the steady-state pharmacokinetics of digoxin administered as a 0.25 mg daily dose in 18 smokers.

Warfarin

Varenicline (1 mg twice daily) did not alter the pharmacokinetics of a single 25 mg dose of (R, S)-warfarin in 24 smokers. Prothrombin time (INR) was not affected by varenicline. Smoking cessation itself may result in changes to warfarin pharmacokinetics [see Drug Interactions (7.2)].

Use with Other Drugs for Smoking Cessation

Bupropion: Varenicline (1 mg twice daily) did not alter the steady-state pharmacokinetics of bupropion (150 mg twice daily) in 46 smokers [see Drug Interactions (7.1)].

NRT: Although co-administration of varenicline (1 mg twice daily) and transdermal nicotine (21 mg/day) for up to 12 days did not affect nicotine pharmacokinetics, the incidence of adverse reactions was greater for the combination than for NRT alone [see Drug Interactions (7.1)].

13 NONCLINICAL TOXICOLOGY

13.1 Carcinogenesis, Mutagenesis, Impairment of Fertility

Carcinogenesis

Lifetime carcinogenicity studies were performed in CD-1 mice and Sprague-Dawley rats. There was no evidence of a carcinogenic effect in mice administered varenicline by oral gavage for 2 years at doses up to 20 mg/kg/day (47 times the maximum recommended human daily (MRHD) exposure based on AUC). Rats were administered varenicline (1, 5, and 15 mg/kg/day) by oral gavage for 2 years. In male rats (n = 65 per sex per dose group), incidences of hibernoma (tumor of the brown fat) were increased at the mid dose (1 tumor, 5 mg/kg/day, 23 times the MRHD exposure based on AUC) and maximum dose (2 tumors, 15 mg/kg/day, 67 times the MRHD exposure based on AUC). The clinical relevance of this finding to humans has not been established. There was no evidence of carcinogenicity in female rats.

Mutagenesis

Varenicline was not genotoxic, with or without metabolic activation, in the following assays: Ames bacterial mutation assay; mammalian CHO/HGPRT assay; and tests for cytogenetic aberrations in vivo in rat bone marrow and in vitro in human lymphocytes.

Impairment of Fertility

There was no evidence of impairment of fertility in either male or female Sprague-Dawley rats administered varenicline succinate up to 15 mg/kg/day (67 and 36 times, respectively, the MRHD exposure based on AUC at 1 mg twice daily). Maternal toxicity, characterized by a decrease in body weight gain, was observed at 15 mg/kg/day. However, a decrease in fertility was noted in the offspring of pregnant rats who were administered varenicline succinate at an oral dose of 15 mg/kg/day. This decrease in fertility in the offspring of treated female rats was not evident at an oral dose of 3 mg/kg/day (9 times the MRHD exposure based on AUC at 1 mg twice daily).

14 CLINICAL STUDIES

The efficacy of CHANTIX in smoking cessation was demonstrated in six clinical trials in which a total of 3659 chronic cigarette smokers (≥10 cigarettes per day) were treated with CHANTIX. In all clinical studies, abstinence from smoking was determined by patient self-report and verified by measurement of exhaled carbon monoxide (CO≤10 ppm) at weekly visits. Among the CHANTIX-treated patients enrolled in these studies, the completion rate was 65%. Except for the dose-ranging study (Study 1) and the maintenance of abstinence study (Study 6), patients were treated for 12 weeks and then were followed for 40 weeks post-treatment. Most patients enrolled in these trials were white (79–96%). All studies enrolled almost equal numbers of men and women. The average age of patients in these studies was 43 years. Patients on average had smoked about 21 cigarettes per day for an average of approximately 25 years. Patients set a date to stop smoking (target quit date) with dosing starting 1 week before this date.

Seven additional studies evaluated the efficacy of CHANTIX in patients with cardiovascular disease, in patients with chronic obstructive pulmonary disease [see Clinical Studies (14.7)], in patients instructed to select their quit date within days 8 and 35 of treatment [see Clinical Studies (14.4)], patients with major depressive disorder [see Clinical Studies (14.9)], patients who had made a previous attempt to quit smoking with CHANTIX, and either did not succeed in quitting or relapsed after treatment [see Clinical Studies (14.6)], in patients without or with a history of psychiatric disorder enrolled in a postmarketing neuropsychiatric safety outcome trial [see Warnings and Precautions (5.1), Clinical Studies (14.10)], and in patients who were not able or willing to quit abruptly and were instructed to quit gradually [see Clinical studies (14.5)].

In all studies, patients were provided with an educational booklet on smoking cessation and received up to 10 minutes of smoking cessation counseling at each weekly treatment visit according to Agency for Healthcare Research and Quality guidelines.

14.1 Initiation of Abstinence

Study 1

This was a six-week dose-ranging study comparing CHANTIX to placebo. This study provided initial evidence that CHANTIX at a total dose of 1 mg per day or 2 mg per day was effective as an aid to smoking cessation.

Study 2

This study of 627 patients compared CHANTIX 1 mg per day and 2 mg per day with placebo. Patients were treated for 12 weeks (including one-week titration) and then were followed for 40 weeks post-treatment. CHANTIX was given in two divided doses daily. Each dose of CHANTIX was given in two different regimens, with and without initial dose-titration, to explore the effect of different dosing regimens on tolerability. For the titrated groups, dosage was titrated up over the course of one week, with full dosage achieved starting with the second week of dosing. The titrated and nontitrated groups were pooled for efficacy analysis.

Forty-five percent of patients receiving CHANTIX 1 mg per day (0.5 mg twice daily) and 51% of patients receiving 2 mg per day (1 mg twice daily) had CO-confirmed continuous abstinence during weeks 9 through 12 compared to 12% of patients in the placebo group (Figure 1). In addition, 31% of the 1 mg per day group and 31% of the 2 mg per day group were continuously abstinent from one week after TQD through the end of treatment as compared to 8% of the placebo group.

Study 3

This flexible-dosing study of 312 patients examined the effect of a patient-directed dosing strategy of CHANTIX or placebo. After an initial one-week titration to a dose of 0.5 mg twice daily, patients could adjust their dosage as often as they wished between 0.5 mg once daily to 1 mg twice daily per day. Sixty-nine percent of patients titrated to the maximum allowable dose at any time during the study. For 44% of patients, the modal dose selected was 1 mg twice daily; for slightly over half of the study participants, the modal dose selected was 1 mg/day or less.

Of the patients treated with CHANTIX, 40% had CO-confirmed continuous abstinence during weeks 9 through 12 compared to 12% in the placebo group. In addition, 29% of the CHANTIX group were continuously abstinent from one week after TQD through the end of treatment as compared to 9% of the placebo group.

Study 4 and Study 5

These identical double-blind studies compared CHANTIX 2 mg per day, bupropion sustained-release (SR) 150 mg twice daily, and placebo. Patients were treated for 12 weeks and then were followed for 40 weeks post-treatment. The CHANTIX dosage of 1 mg twice daily was achieved using a titration of 0.5 mg once daily for the initial 3 days followed by 0.5 mg twice daily for the next 4 days. The bupropion SR dosage of 150 mg twice daily was achieved using a 3-day titration of 150 mg once daily. Study 4 enrolled 1022 patients and Study 5 enrolled 1023 patients. Patients inappropriate for bupropion treatment or patients who had previously used bupropion were excluded.

In Study 4, patients treated with CHANTIX had a superior rate of CO-confirmed abstinence during weeks 9 through 12 (44%) compared to patients treated with bupropion SR (30%) or placebo (17%). The bupropion SR quit rate was also superior to placebo. In addition, 29% of the CHANTIX group were continuously abstinent from one week after TQD through the end of treatment as compared to 12% of the placebo group and 23% of the bupropion SR group.

Similarly in Study 5, patients treated with CHANTIX had a superior rate of CO-confirmed abstinence during weeks 9 through 12 (44%) compared to patients treated with bupropion SR (30%) or placebo (18%). The bupropion SR quit rate was also superior to placebo. In addition, 29% of the CHANTIX group were continuously abstinent from one week after TQD through the end of treatment as compared to 11% of the placebo group and 21% of the bupropion SR group.

Figure 1: Continuous Abstinence, Weeks 9 through 12

Table 7. Continuous Abstinence, Weeks 9 through 12 (95% confidence interval)
 | CHANTIX 0.5 mg BID | CHANTIX 1 mg BID | CHANTIX Flexible | Bupropion SR | Placebo
Study 2 | 45% (39%, 51%) | 51% (44%, 57%) |  |  | 12% (6%, 18%)
Study 3 |  |  | 40% (32%, 48%) |  | 12% (7%, 17%)
Study 4 |  | 44% (38%, 49%) |  | 30% (25%, 35%) | 17% (13%, 22%)
Study 5 |  | 44% (38%, 49%) |  | 30% (25%, 35%) | 18% (14%, 22%)
BID = twice daily

14.2 Urge to Smoke

Based on responses to the Brief Questionnaire of Smoking Urges and the Minnesota Nicotine Withdrawal scale "urge to smoke" item, CHANTIX reduced urge to smoke compared to placebo.

14.3 Long-Term Abstinence

Studies 1 through 5 included 40 weeks of post-treatment follow-up. In each study, CHANTIX-treated patients were more likely to maintain abstinence throughout the follow-up period than were patients treated with placebo (Figure 2, Table 8).

Figure 2: Continuous Abstinence, Weeks 9 through 52

Table 8. Continuous Abstinence, Weeks 9 through 52 (95% confidence interval) Across Different Studies
 | CHANTIX 0.5 mg BID | CHANTIX 1 mg BID | CHANTIX Flexible | Bupropion SR | Placebo
Study 2 | 19% (14%, 24%) | 23% (18%, 28%) |  |  | 4% (1%, 8%)
Study 3 |  |  | 22% (16%, 29%) |  | 8% (3%, 12%)
Study 4 |  | 21% (17%, 26%) |  | 16% (12%, 20%) | 8% (5%, 11%)
Study 5 |  | 22% (17%, 26%) |  | 14% (11%, 18%) | 10% (7%, 13%)
BID = twice daily

Study 6

This study assessed the effect of an additional 12 weeks of CHANTIX therapy on the likelihood of long-term abstinence. Patients in this study (N=1927) were treated with open-label CHANTIX 1 mg twice daily for 12 weeks. Patients who had stopped smoking for at least a week by Week 12 (N= 1210) were then randomized to double-blind treatment with CHANTIX (1 mg twice daily) or placebo for an additional 12 weeks and then followed for 28 weeks post-treatment.

The Continuous Abstinence Rate from Week 13 through Week 24 was higher for patients continuing treatment with CHANTIX (70%) than for patients switching to placebo (50%). Superiority to placebo was also maintained during 28 weeks post-treatment follow-up (CHANTIX 54% versus placebo 39%).

In Figure 3 below, the x-axis represents the study week for each observation, allowing a comparison of groups at similar times after discontinuation of CHANTIX; post-CHANTIX follow-up begins at Week 13 for the placebo group and Week 25 for the CHANTIX group. The y-axis represents the percentage of patients who had been abstinent for the last week of CHANTIX treatment and remained abstinent at the given timepoint.

Figure 3: Continuous Abstinence Rate during Nontreatment Follow-Up

14.4 Alternative Instructions for Setting a Quit Date

CHANTIX was evaluated in a double-blind, placebo-controlled trial where patients were instructed to select a target quit date between Day 8 and Day 35 of treatment. Subjects were randomized 3:1 to CHANTIX 1 mg twice daily (N=486) or placebo (N=165) for 12 weeks of treatment and followed for another 12 weeks post-treatment. Patients treated with CHANTIX had a superior rate of CO-confirmed abstinence during weeks 9 through 12 (54%) compared to patients treated with placebo (19%) and from weeks 9 through 24 (35%) compared to subjects treated with placebo (13%).

14.5 Gradual Approach to Quitting Smoking

CHANTIX was evaluated in a 52-week double-blind placebo-controlled study of 1,510 subjects who were not able or willing to quit smoking within four weeks, but were willing to gradually reduce their smoking over a 12 week period before quitting. Subjects were randomized to either CHANTIX 1 mg twice daily (N=760) or placebo (N=750) for 24 weeks and followed up post-treatment through week 52. Subjects were instructed to reduce the number of cigarettes smoked by at least 50 percent by the end of the first four weeks of treatment, followed by a further 50 percent reduction from week four to week eight of treatment, with the goal of reaching complete abstinence by 12 weeks. After the initial 12-week reduction phase, subjects continued treatment for another 12 weeks. Subjects treated with CHANTIX had a significantly higher Continuous Abstinence Rate compared with placebo at weeks 15 through 24 (32% vs. 7%) and weeks 15 through 52 (24% vs. 6%).

14.6 Re-Treatment Study

CHANTIX was evaluated in a double-blind, placebo-controlled trial of patients who had made a previous attempt to quit smoking with CHANTIX, and either did not succeed in quitting or relapsed after treatment. Subjects were randomized 1:1 to CHANTIX 1 mg twice daily (N=249) or placebo (N=245) for 12 weeks of treatment and followed for 40 weeks post-treatment. Patients included in this study had taken CHANTIX for a smoking-cessation attempt in the past (for a total treatment duration of a minimum of two weeks), at least three months prior to study entry, and had been smoking for at least four weeks.

Patients treated with CHANTIX had a superior rate of CO-confirmed abstinence during weeks 9 through 12 (45%) compared to patients treated with placebo (12%) and from weeks 9 through 52 (20%) compared to subjects treated with placebo (3%).

Table 9. Continuous Abstinence (95% confidence interval), Re-Treatment Study
 | Weeks 9 through 12 |  | Weeks 9 through 52
 | CHANTIX 1 mg BID | Placebo | CHANTIX 1 mg BID | Placebo
Re-treatment Study | 45% (39%, 51%) | 12% (8%, 16%) | 20% (15%, 25%) | 3% (1%, 5%)
BID = twice daily

14.7 Subjects with Chronic Obstructive Pulmonary Disease

CHANTIX was evaluated in a randomized, double-blind, placebo-controlled study of subjects aged ≥ 35 years with mild-to-moderate COPD with post-bronchodilator FEV1/FVC <70% and FEV1 ≥ 50% of predicted normal value. Subjects were randomized to CHANTIX 1 mg twice daily (N=223) or placebo (N=237) for a treatment of 12 weeks and then were followed for 40 weeks post-treatment. Subjects treated with CHANTIX had a superior rate of CO-confirmed abstinence during weeks 9 through 12 (41%) compared to subjects treated with placebo (9%) and from week 9 through 52 (19%) compared to subjects treated with placebo (6%).

Table 10. Continuous Abstinence (95% confidence interval), Studies in Patients with Chronic Obstructive Pulmonary Disease (COPD)
 | Weeks 9 through 12 |  | Weeks 9 through 52
 | CHANTIX 1 mg BID | Placebo | CHANTIX 1 mg BID | Placebo
COPD Study | 41% (34%, 47%) | 9% (6%, 13%) | 19% (14%, 24%) | 6% (3%, 9%)
BID = twice daily

14.8 Subjects with Cardiovascular Disease and Other Cardiovascular Analyses

CHANTIX was evaluated in a randomized, double-blind, placebo-controlled study of subjects aged 35 to 75 years with stable, documented cardiovascular disease (diagnoses other than, or in addition to, hypertension) that had been diagnosed for more than 2 months. Subjects were randomized to CHANTIX 1 mg twice daily (N=353) or placebo (N=350) for a treatment period of 12 weeks and then were followed for 40 weeks post-treatment. Subjects treated with CHANTIX had a superior rate of CO-confirmed abstinence during weeks 9 through 12 (47%) compared to subjects treated with placebo (14%) and from week 9 through 52 (20%) compared to subjects treated with placebo (7%).

Table 11. Continuous Abstinence (95% confidence interval), Studies in Patients with Cardiovascular Disease (CVD)
 | Weeks 9 through 12 |  | Weeks 9 through 52
 | CHANTIX 1 mg BID | Placebo | CHANTIX 1 mg BID | Placebo
CVD Study | 47% (42%, 53%) | 14% (11%, 18%) | 20% (16%, 24%) | 7% (5%, 10%)
BID = twice daily

In this study, all-cause and CV mortality was lower in patients treated with CHANTIX, but certain nonfatal CV events occurred more frequently in patients treated with CHANTIX than in patients treated with placebo [see Warnings and Precautions (5.5), Adverse Reactions (6.1)]. Table 12 below shows mortality and the incidence of selected nonfatal serious CV events occurring more frequently in the CHANTIX arm compared to the placebo arm. These events were adjudicated by an independent blinded committee. Nonfatal serious CV events not listed occurred at the same incidence or more commonly in the placebo arm. Patients with more than one CV event of the same type are counted only once per row. Some of the patients requiring coronary revascularization underwent the procedure as part of management of nonfatal MI and hospitalization for angina.

Table 12. Mortality and Adjudicated Nonfatal Serious Cardiovascular Events in the Placebo-Controlled CHANTIX Trial in Patients with Stable Cardiovascular Disease
Mortality and Cardiovascular Events | CHANTIX (N=353) n (%) | Placebo (N=350) n (%)
Mortality (Cardiovascular and All-cause up to 52 weeks)
Cardiovascular | 1 (0.3) | 2 (0.6)
All-cause | 2 (0.6) | 5 (1.4)
Nonfatal Cardiovascular Events (rate on CHANTIX > Placebo)
Up to 30 days after treatment
Nonfatal myocardial infarction | 4 (1.1) | 1 (0.3)
Nonfatal Stroke | 2 (0.6) | 0 (0)
Beyond 30 days after treatment and up to 52 weeks
Nonfatal myocardial infarction | 3 (0.8) | 2 (0.6)
Need for coronary revascularization | 7 (2.0) | 2 (0.6)
Hospitalization for angina pectoris | 6 (1.7) | 4 (1.1)
Transient ischemia attack | 1 (0.3) | 0 (0)
New diagnosis of peripheral vascular disease (PVD) or admission for a PVD procedure | 5 (1.4) | 2 (0.6)

Following the CVD study, a meta-analysis of 15 clinical trials of ≥12 weeks treatment duration, including 7002 patients (4190 CHANTIX, 2812 placebo), was conducted to systematically assess the CV safety of CHANTIX. The study in patients with stable CV disease described above was included in the meta-analysis. There were lower rates of all-cause mortality (CHANTIX 6 [0.14%]; placebo 7 [0.25%]) and CV mortality (CHANTIX 2 [0.05%]; placebo 2 [0.07%]) in the CHANTIX arms compared with the placebo arms in the meta-analysis.

The key CV safety analysis included occurrence and timing of a composite endpoint of Major Adverse Cardiovascular Events (MACE), defined as CV death, nonfatal MI, and nonfatal stroke. These events included in the endpoint were adjudicated by a blinded, independent committee. Overall, a small number of MACE occurred in the trials included in the meta-analysis, as described in Table 13. These events occurred primarily in patients with known CV disease.

Table 13. Number of MACE cases, Hazard Ratio and Rate Difference in a Meta-Analysis of 15 Clinical Trials Comparing CHANTIX to Placebo [Includes MACE occurring up to 30 days post-treatment.]
 | CHANTIX N=4190 | Placebo N=2812
MACE cases, n (%) | 13 (0.31%) | 6 (0.21%)
Patient-years of exposure | 1316 | 839
Hazard Ratio (95% CI)
 | 1.95 (0.79, 4.82)
Rate Difference per 1,000 patient-years (95% CI)
 | 6.30 (-2.40, 15.10)

The meta-analysis showed that exposure to CHANTIX resulted in a hazard ratio for MACE of 1.95 (95% confidence interval from 0.79 to 4.82) for patients up to 30 days after treatment; this is equivalent to an estimated increase of 6.3 MACE events per 1,000 patient-years of exposure. The meta-analysis showed higher rates of CV endpoints in patients on CHANTIX relative to placebo across different time frames and pre-specified sensitivity analyses, including various study groupings and CV outcomes. Although these findings were not statistically significant they were consistent. Because the number of events was small overall, the power for finding a statistically significant difference in a signal of this magnitude is low.

Additionally, a cardiovascular endpoint analysis was added to the postmarketing neuropsychiatric safety outcome study along with a non-treatment extension, [see Warnings and Precautions (5.5), Adverse Reactions (6.1), Clinical Studies (14.10)].

14.9 Subjects with Major Depressive Disorder

CHANTIX was evaluated in a randomized, double-blind, placebo-controlled study of subjects aged 18 to 75 years with major depressive disorder without psychotic features (DSM-IV TR). If on medication, subjects were to be on a stable antidepressant regimen for at least two months. If not on medication, subjects were to have experienced a major depressive episode in the past 2 years, which was successfully treated. Subjects were randomized to CHANTIX 1 mg twice daily (N=256) or placebo (N=269) for a treatment of 12 weeks and then followed for 40 weeks post-treatment. Subjects treated with CHANTIX had a superior rate of CO-confirmed abstinence during weeks 9 through 12 (36%) compared to subjects treated with placebo (16%) and from week 9 through 52 (20%) compared to subjects treated with placebo (10%).

Table 14. Continuous Abstinence (95% confidence interval), Study in Patients with Major Depressive Disorder (MDD)
 | Weeks 9 through 12 |  | Weeks 9 through 52
 | CHANTIX 1 mg BID | Placebo | CHANTIX 1 mg BID | Placebo
MDD Study | 36% (30%, 42%) | 16% (11%, 20%) | 20% (15%, 25%) | 10% (7%, 14%)
BID = twice daily

14.10 Postmarketing Neuropsychiatric Safety Outcome Trial

CHANTIX was evaluated in a randomized, double-blind, active and placebo-controlled trial that included subjects without a history of psychiatric disorder (non-psychiatric cohort, N=3912) and with a history of psychiatric disorder (psychiatric cohort, N=4003). Subjects aged 18–75 years, smoking 10 or more cigarettes per day were randomized 1:1:1:1 to CHANTIX 1 mg BID, bupropion SR 150 mg BID, NRT patch 21 mg/day with taper or placebo for a treatment period of 12 weeks; they were then followed for another 12 weeks post-treatment. [See Warnings and Precautions (5.1)]

A composite safety endpoint intended to capture clinically significant neuropsychiatric (NPS) adverse events included the following NPS adverse events: anxiety, depression, feeling abnormal, hostility, agitation, aggression, delusions, hallucinations, homicidal ideation, mania, panic, paranoia, psychosis, irritability, suicidal ideation, suicidal behavior or completed suicide.

As shown in Table 15, the use of CHANTIX, bupropion, and NRT in the non-psychiatric cohort was not associated with an increased risk of clinically significant NPS adverse events compared with placebo. Similarly, in the non-psychiatric cohort, the use of CHANTIX was not associated with an increased risk of clinically significant NPS adverse events in the composite safety endpoint compared with bupropion or NRT.

Table 15. Number of Patients with Clinically Significant or Serious NPS Adverse Events by Treatment Group Among Patients without a History of Psychiatric Disorder
 | CHANTIX (N=975) n (%) | Bupropion (N=968) n (%) | NRT (N=987) n (%) | Placebo (N=982) n (%)
Clinically Significant NPS | 30 (3.1) | 34 (3.5) | 33 (3.3) | 40 (4.1)
Serious NPS | 1 (0.1) | 5 (0.5) | 1 (0.1) | 4 (0.4)
Psychiatric Hospitalizations | 1 (0.1) | 2 (0.2) | 0 (0.0) | 1 (0.1)

As shown in Table 16, there were more clinically significant NPS adverse events reported in patients in the psychiatric cohort in each treatment group compared with the non-psychiatric cohort. The incidence of events in the composite endpoint was higher for each of the active treatments compared to placebo: Risk Differences (RDs) (95%CI) vs placebo were 2.7% (-0.05, 5.4) for CHANTIX, 2.2% (-0.5, 4.9) for bupropion, and 0.4% (-2.2, 3.0) for NRT transdermal nicotine.

Table 16. Number of Patients with Clinically Significant or Serious NPS Adverse Events by Treatment Group Among Patients with a History of Psychiatric Disorder
 | CHANTIX (N=1007) n (%) | Bupropion (N=1004) n (%) | NRT (N=995) n (%) | Placebo (N=997) n (%)
Clinically Significant NPS | 123 (12.2) | 118 (11.8) | 98 (9.8) | 95 (9.5)
Serious NPS | 6 (0.6) | 8 (0.8) | 4 (0.4) | 6 (0.6)
Psychiatric hospitalizations | 5 (0.5) | 8 (0.8) | 4 (0.4) | 2 (0.2)

There was one completed suicide, which occurred during treatment in a patient treated with placebo in the non-psychiatric cohort. There were no completed suicides reported in the psychiatric cohort.

In both cohorts, subjects treated with CHANTIX had a superior rate of CO-confirmed abstinence during weeks 9 through 12 and 9 through 24 compared to subjects treated with bupropion, nicotine patch and placebo.

Table 17 Continuous Abstinence (95% confidence interval), Study in Patients with or without a History of Psychiatric Disorder
 | CHANTIX 1 mg BID | Bupropion SR 150 mg BID | NRT 21 mg/day with taper | Placebo
Weeks 9 through 12
Non-Psychiatric Cohort | 38% (35%, 41%) | 26% (23%, 29%) | 26% (24%, 29%) | 14% (12%, 16%)
Psychiatric Cohort | 29% (26%, 32%) | 19% (17%, 22%) | 20% (18%, 23%) | 11% (10%, 14%)
Weeks 9 through 24
Non-Psychiatric Cohort | 25% (23%, 28%) | 19% (16%, 21%) | 18% (16%, 21%) | 11% (9%, 13%)
Psychiatric Cohort | 18% (16%, 21%) | 14% (12%, 16%) | 13% (11%, 15%) | 8% (7%, 10%)
BID = twice daily

Cardiovascular Outcome Analysis

To obtain another source of data regarding the CV risk of CHANTIX, a cardiovascular endpoint analysis was added to the postmarketing neuropsychiatric safety outcome study along with a non-treatment extension. In the parent study (N=8027), subjects aged 18–75 years, smoking 10 or more cigarettes per day were randomized 1:1:1:1 to CHANTIX 1 mg BID, bupropion SR 150 mg BID, nicotine replacement therapy (NRT) patch 21 mg/day or placebo for a treatment period of 12 weeks; they were then followed for another 12 weeks post-treatment. The extension study enrolled 4590 (57.2%) of the 8027 subjects who were randomized and treated in the parent study and followed them for additional 28 weeks. Of all treated subjects, 1743 (21.7%) had a medium CV risk and 640 (8.0%) had a high CV risk, as defined by Framingham score. Note that one site from the parent study was excluded in the assessment of CV safety and two sites were excluded in the assessment of neuropsychiatric safety.

The primary CV endpoint was the time to major adverse CV event (MACE), defined as CV death, nonfatal myocardial infarction or nonfatal stroke during treatment. Deaths and CV events were adjudicated by a blinded, independent committee. Table 18 below shows the incidence of MACE and Hazard Ratios compared to placebo for all randomized subjects exposed to at least 1 partial dose of study treatment in the parent study.

Table 18. The Incidence of MACE and Hazard Ratios in the Cardiovascular Safety Assessment Trial in Subjects without or with a History of Psychiatric Disorder
 | CHANTIX N=2006 | Bupropion N=1997 | NRT N=2017 | Placebo N=2007
During treatment [during treatment in the parent neuropsychiatric safety study]
MACE, n [IR] | 1 [2.4] | 2 [4.9] | 1 [2.4] | 4 [9.8]
Hazard Ratio (95% CI) vs. placebo | 0.24 (0.03, 2.18) | 0.49 (0.09, 2.69) | 0.24 (0.03, 2.18)
Through end of study [either the end of the extension study or the end of parent neuropsychiatric safety study for those subjects not enrolled into the extension study]
MACE, n [IR] | 3 [2.1] | 9 [6.3] | 6 [4.3] | 8 [5.7]
Hazard Ratio (95% CI) vs. placebo | 0.36 (0.10, 1.36) | 1.09 (0.42, 2.83) | 0.74 (0.26, 2.13)
[IR] indicates incidence rate per 1000 person-years

For this study, MACE+ was defined as any MACE or a new onset or worsening peripheral vascular disease (PVD) requiring intervention, a need for coronary revascularization, or hospitalization for unstable angina. Incidence rates of MACE+ and all-cause mortality for all randomized subjects exposed to at least 1 partial dose of study treatment in the parent study are shown for all treatment groups during treatment, and through end of study in the Table 19 below.

Table 19. The Incidence of MACE+ and All-Cause Death in the Cardiovascular Safety Assessment Trial in Subjects without or with a History of Psychiatric Disorder
 | CHANTIX N=2006 | Bupropion N=1997 | NRT N=2017 | Placebo N=2007
During treatment [during treatment in the parent neuropsychiatric safety study]
MACE+, n [IR] | 5 [12.1] | 4 [9.9] | 2 [4.8] | 5 [12.2]
All-cause deaths, n [IR] | 0 | 2 [4.9] | 0 | 2 [4.9]
Through end of study [either the end of the extension study or the end of the parent neuropsychiatric safety study for those subjects not enrolled into the extension study]
MACE+, n [IR] | 10 [6.9] | 15 [10.5] | 10 [7.1] | 12 [8.6]
All-cause deaths, n [IR] | 2 [1.4] | 4 [2.8] | 3 [2.1] | 4 [2.9]
[IR] indicates incidence rate per 1000 person-years

The number of subjects who experienced MACE, MACE+ and all-cause death was similar or lower among patients treated with CHANTIX than patients treated with placebo. The number of events observed overall was too low to distinguish meaningful differences between the treatment arms.

16 HOW SUPPLIED/STORAGE AND HANDLING

CHANTIX is supplied for oral administration in two strengths: a 0.5 mg capsular biconvex, white to off-white, film-coated tablet debossed with "Pfizer" on one side and "CHX 0.5" on the other side and a 1 mg capsular biconvex, light blue film-coated tablet debossed with "Pfizer" on one side and "CHX 1.0" on the other side. CHANTIX is supplied in the following package configurations:

 | Description | NDC
Packs | Starting 4-week card: 0.5 mg × 11 tablets and 1 mg × 42 tablets | NDC 0069-0471-28
 | Continuing 4-week card: 1 mg × 56 tablets | NDC 0069-0469-28
Bottles | 0.5 mg - bottle of 56 | NDC 0069-0468-56
Bottles | 1 mg - bottle of 56 | NDC 0069-0469-56

STORAGE AND HANDLING

Store at 25ºC (77ºF); excursions permitted to 15ºC to 30ºC (59ºF to 86ºF) (see USP Controlled Room Temperature).

17 PATIENT COUNSELING INFORMATION

See FDA-approved patient labeling (Medication Guide)

Initiate Treatment and Continue to Attempt to Quit if Lapse

Instruct patients to set a date to quit smoking and to initiate CHANTIX treatment one week before the quit date. Alternatively, the patient can begin CHANTIX dosing and then set a date to quit smoking between days 8 and 35 of treatment. Encourage patients to continue to attempt to quit if they have early lapses after quit day [see Dosage and Administration (2.1)].

For patients who are sure that they are not able or willing to quit abruptly, a gradual approach to quitting smoking with CHANTIX may be considered. Patients should begin CHANTIX dosing and reduce smoking during the first 12 weeks of treatment, then quit by the end of that period and continue treatment for an additional 12 weeks for a total of 24 weeks [see Dosage and Administration (2.1)].

Encourage patients who are motivated to quit and who did not succeed in stopping smoking during prior CHANTIX therapy for reasons other than intolerability due to adverse events, or who relapsed after treatment to make another attempt with CHANTIX once factors contributing to the failed attempt have been identified and addressed [see Dosage and Administration (2.1), Clinical Studies (14.6)].

How to Take

Advise patients that CHANTIX should be taken orally after eating, and with a full glass of water [see Dosage and Administration (2.1)].

Starting Week Dosage

Instruct patients on how to titrate CHANTIX, beginning at a dose of 0.5 mg/day. Explain that one 0.5 mg tablet should be taken daily for the first three days, and that for the next four days, one 0.5 mg tablet should be taken in the morning and one 0.5 mg tablet should be taken in the evening [see Dosage and Administration (2.1)].

Continuing Weeks Dosage

Advise patients that, after the first seven days, the dose should be increased to one 1 mg tablet in the morning and one 1 mg tablet in the evening [see Dosage and Administration (2.1)].

Dosage Adjustment for CHANTIX or Other Drugs

Inform patients that nausea and insomnia are side effects of CHANTIX and are usually transient; however, advise patients that if they are persistently troubled by these symptoms, they should notify the prescribing physician so that a dose reduction can be considered.

Inform patients that some drugs may require dose adjustment after quitting smoking [see Dosage and Administration (2.1)].

Counseling and Support

Provide patients with educational materials and necessary counseling to support an attempt at quitting smoking [see Dosage and Administration (2.1)].

Neuropsychiatric Adverse Events

Inform patients that some patients have experienced changes in mood (including depression and mania), psychosis, hallucinations, paranoia, delusions, homicidal ideation, aggression, hostility, agitation, anxiety, and panic, as well as suicidal ideation and suicide when attempting to quit smoking while taking CHANTIX. Instruct patients to discontinue CHANTIX and contact a healthcare professional if they experience such symptoms [see Warnings and Precautions (5.1), Adverse Reactions (6.2)].

History of Psychiatric Illness

Encourage patients to reveal any history of psychiatric illness prior to initiating treatment.

Nicotine Withdrawal

Inform patients that quitting smoking, with or without CHANTIX, may be associated with nicotine withdrawal symptoms (including depression or agitation) or exacerbation of pre-existing psychiatric illness.

Seizures

Encourage patients to report any history of seizures or other factors that can lower seizure threshold. Instruct patients to discontinue CHANTIX and contact a healthcare provider immediately if they experience a seizure while on treatment [see Warnings and Precautions (5.2)].

Interaction with Alcohol

Advise patients to reduce the amount of alcohol they consume while taking CHANTIX until they know whether CHANTIX affects their tolerance for alcohol [see Warnings and Precautions (5.3), Adverse Reactions (6.2)].

Driving or Operating Machinery

Advise patients to use caution driving or operating machinery until they know how quitting smoking and/or varenicline may affect them [see Warnings and Precautions (5.4)].

Cardiovascular Events

Patients should be instructed to notify their healthcare providers of symptoms of new or worsening cardiovascular events and to seek immediate medical attention if they experience signs and symptoms of myocardial infarction or stroke [see Warnings and Precautions (5.5), Adverse Reactions (6.1)].

Somnambulism

Patients should be instructed to discontinue CHANTIX and notify their healthcare providers if they experience somnambulism [see Warnings and Precautions (5.6)].

Angioedema

Inform patients that there have been reports of angioedema, with swelling of the face, mouth (lip, gum, tongue) and neck (larynx and pharynx) that can lead to life-threatening respiratory compromise. Instruct patients to discontinue CHANTIX and immediately seek medical care if they experience these symptoms [see Warnings and Precautions (5.7), Adverse Reactions (6.2)].

Serious Skin Reactions

Inform patients that serious skin reactions, such as Stevens-Johnson Syndrome and erythema multiforme, were reported by some patients taking CHANTIX. Advise patients to stop taking CHANTIX at the first sign of rash with mucosal lesions or skin reaction and contact a healthcare provider immediately [see Warnings and Precautions (5.8), Adverse Reactions (6.2)].

Vivid, Unusual, or Strange Dreams

Inform patients that they may experience vivid, unusual or strange dreams during treatment with CHANTIX.

Pregnancy and Lactation

Patients who are pregnant or breastfeeding or planning to become pregnant should be advised of: the risks of smoking to a pregnant mother and her developing baby, the potential risks of CHANTIX use during pregnancy and breastfeeding, and the benefits of smoking cessation with and without CHANTIX. Advise breastfeeding women to monitor the infant for seizures and vomiting [see Use in Specific Populations (8.1 and 8.2)].

This product's label may have been updated. For full prescribing information, please visit www.pfizer.com.

LAB-0327-26.0

MEDICATION GUIDE
CHANTIX® (CHANT-iks)
(varenicline)
Tablets

What is the most important information I should know about CHANTIX?

When you try to quit smoking, with or without CHANTIX, you may have symptoms that may be due to nicotine withdrawal, including:

- urge to smoke
- depressed mood
- trouble sleeping
- irritability

- frustration
- anger
- feeling anxious
- difficulty concentrating

- restlessness
- decreased heart rate
- increased appetite
- weight gain

Some people have even experienced suicidal thoughts when trying to quit smoking without medication. Sometimes quitting smoking can lead to worsening of mental health problems that you already have, such as depression.

Some people have had serious side effects while taking CHANTIX to help them quit smoking, including:

New or worse mental health problems, such as changes in behavior or thinking, aggression, hostility, agitation, depressed mood, or suicidal thoughts or actions. Some people had these symptoms when they began taking CHANTIX, and others developed them after several weeks of treatment, or after stopping CHANTIX. These symptoms happened more often in people who had a history of mental health problems before taking CHANTIX, than in people without a history of mental health problems.

Stop taking CHANTIX and call your healthcare provider right away if you, your family, or caregiver notice any of these symptoms. Work with your healthcare provider to decide whether you should continue to take CHANTIX. In many people, these symptoms went away after stopping CHANTIX, but in some people symptoms continued after stopping CHANTIX. It is important for you to follow-up with your healthcare provider until your symptoms go away.

Before taking CHANTIX, tell your healthcare provider if you have ever had depression or other mental health problems. You should also tell your healthcare provider about any symptoms you had during other times you tried to quit smoking, with or without CHANTIX.

What is CHANTIX?

CHANTIX is a prescription medicine to help people stop smoking.

Quitting smoking can lower your chances of having lung disease, heart disease or getting certain types of cancer that are related to smoking.

CHANTIX has not been shown to be effective in children 16 years of age and under. CHANTIX should not be used in children 16 years of age and under.

It is not known if CHANTIX is safe and effective when used with other stop smoking medicines.

Who should not take CHANTIX?

Do not take CHANTIX if you have had a serious allergic or skin reaction to CHANTIX. Symptoms may include:

- swelling of the face, mouth (tongue, lips, gums), throat or neck

- trouble breathing

- rash, with peeling skin

- blisters in your mouth

What should I tell my healthcare provider before taking CHANTIX?

See "What is the most important information I should know about CHANTIX?"

Before you take CHANTIX, tell your healthcare provider if you:

- use other treatments to quit smoking. Using CHANTIX with a nicotine patch may cause nausea, vomiting, headache, dizziness, upset stomach, and tiredness to happen more often than if you just use a nicotine patch alone.
- have kidney problems or get kidney dialysis. Your healthcare provider may prescribe a lower dose of CHANTIX for you.
- have a history of seizures.
- drink alcohol.
- have heart or blood vessel problems.
- have any other medical conditions.
- are pregnant or plan to become pregnant.
- are breastfeeding. It is not known if CHANTIX passes into breast milk. If you breastfeed and take CHANTIX, monitor your baby for seizures as well as spitting up or vomiting more than normal.

Tell your healthcare provider about all the medicines you take, including prescription and over-the-counter medicines, vitamins and herbal supplements. Your healthcare provider may need to change the dose of some of your medicines when you stop smoking.

You should not use CHANTIX while using other medicines to quit smoking. Tell your healthcare provider if you use other treatments to quit smoking.

Know the medicines you take. Keep a list of them with you to show your healthcare provider and pharmacist when you get a new medicine.

How should I take CHANTIX?

- There are 3 ways that you can use CHANTIX to help you quit smoking. Talk to your healthcare provider about the following 3 ways to use CHANTIX:
  - Choose a quit date when you will stop smoking. Start taking CHANTIX 1 week (7 days) before your quit date. Take CHANTIX for 12 weeks.
    OR
  - Start taking CHANTIX before you choose a quit date. Pick a date to quit smoking that is between days 8 and 35 of treatment. Take CHANTIX for 12 weeks.
    OR
  - If you are sure that you are not able or willing to quit smoking right away, start taking CHANTIX and reduce smoking during the first 12 weeks of treatment, as follows:

Weeks 1 through 4

Reduce your smoking to reach one-half of your starting daily number of cigarettes.

Example: If you usually smoke 20 cigarettes each day, reduce your smoking to 10 cigarettes each day during weeks 1 through 4.

Weeks 5 through 8

Reduce your smoking to reach one-quarter of your starting daily number of cigarettes.

Example: If you usually smoked 20 cigarettes each day, reduce your smoking to 5 cigarettes each day during weeks 5 through 8.

Weeks 9 through 12

Keep reducing your smoking until you are no longer smoking (you reach zero cigarettes each day).

Aim to quit by the end of the 12th week of treatment, or sooner if you feel ready. Continue to take CHANTIX for another 12 weeks, for a total of 24 weeks of treatment.

Starting CHANTIX before your quit date gives CHANTIX time to build up in your body. You can keep smoking during this time. Take CHANTIX exactly as prescribed by your healthcare provider.

- CHANTIX comes as a white tablet (0.5 mg) and a blue tablet (1 mg). You start with the white tablet and then usually go to the blue tablet. See the chart below for dosing instructions for adults.

Day 1 to Day 3

- White tablet (0.5 mg)
- Take 1 tablet each day

Day 4 to Day 7

- White tablet (0.5 mg)
- Take 1 in the morning and 1 in the evening

Day 8 to end of treatment

- Blue tablet (1 mg)
- Take 1 in the morning and 1 in the evening

- Make sure that you try to stop smoking on your quit date. If you slip-up and smoke, try again. Some people need to take CHANTIX for a few weeks for CHANTIX to work best.
- Most people will take CHANTIX for up to 12 weeks. If you have completely quit smoking by 12 weeks, your healthcare provider may prescribe CHANTIX for another 12 weeks to help you stay cigarette-free.
- Take CHANTIX after eating and with a full glass (8 ounces) of water.
- This dosing schedule may not be right for everyone. Talk to your healthcare provider if you are having side effects such as nausea, strange dreams, or sleep problems. Your healthcare provider may want to reduce your dose.
- If you miss a dose of CHANTIX, take it as soon as you remember. If it is almost time for your next dose, skip the missed dose. Just take your next dose at your regular time.

What should I avoid while taking CHANTIX?

- Use caution when driving or operating machinery until you know how CHANTIX affects you. CHANTIX may make you feel sleepy, dizzy, or have trouble concentrating, making it hard to drive or perform other activities safely.
- Decrease the amount of alcoholic beverages that you drink during treatment with CHANTIX until you know if CHANTIX affects your ability to tolerate alcohol. Some people have experienced the following when drinking alcohol during treatment with CHANTIX:

- increased drunkenness (intoxication)

- unusual or sometimes aggressive behavior
- no memory of things that have happened

What are the possible side effects of CHANTIX?

Serious side effects of CHANTIX may include:

- See "What is the most important information I should know about CHANTIX?"
- Seizures. Some people have had seizures during treatment with CHANTIX. In most cases, the seizures have happened during the first month of treatment with CHANTIX. If you have a seizure during treatment with CHANTIX, stop taking CHANTIX and contact your healthcare provider right away.
- New or worse heart or blood vessel (cardiovascular) problems, mostly in people, who already have cardiovascular problems. Tell your healthcare provider if you have any changes in symptoms during treatment with CHANTIX.
  Get emergency medical help right away if you have any of the following symptoms of a heart attack, including:
  - chest discomfort (uncomfortable pressure, squeezing, fullness or pain) that lasts more than a few minutes, or that goes away and comes back
  - pain or discomfort in one or both arms, back, neck, jaw or stomach
  - shortness of breath, sweating, nausea, vomiting, or feeling lightheaded associated with chest discomfort
- Sleepwalking can happen with CHANTIX, and can sometimes lead to behavior that is harmful to you or other people, or to property. Stop taking CHANTIX and tell your healthcare provider if you start sleepwalking.
- Allergic reactions can happen with CHANTIX. Some of these allergic reactions can be life-threatening.
- Serious skin reactions, including rash, swelling, redness, and peeling of the skin. Some of these skin reactions can become life-threatening.

Stop taking CHANTIX and get medical help right away if you have any of the following symptoms:

- swelling of the face, mouth (tongue, lips, and gums), throat or neck
- trouble breathing
- rash with peeling skin
- blisters in your mouth

The most common side effects of CHANTIX include:

- nausea
- sleep problems (trouble sleeping or vivid, unusual, or strange dreams)
- constipation
- gas
- vomiting

Tell your healthcare provider about side effects that bother you or that do not go away.

These are not all the side effects of CHANTIX. Ask your healthcare provider or pharmacist for more information.

Call your doctor for medical advice about side effects. You may report side effects to FDA at 1-800-FDA-1088.

How should I store CHANTIX?

- Store CHANTIX at room temperature, between 68°F to 77°F (20°C to 25°C).
- Keep CHANTIX and all medicines out of the reach of children.

General information about the safe and effective use of CHANTIX

Medicines are sometimes prescribed for purposes other than those listed in a Medication Guide. Do not use CHANTIX for a condition for which it was not prescribed. Do not give your CHANTIX to other people, even if they have the same symptoms that you have. It may harm them. If you would like more information, talk with your healthcare provider. You can ask your healthcare provider or pharmacist for information about CHANTIX that is written for healthcare professionals.

For more information about CHANTIX and tips on how to quit smoking, go to www.CHANTIX.com or call 1-877-242-6849.

If you are motivated to quit smoking and did not succeed during prior CHANTIX treatment for reasons other than side effects, or if you returned to smoking after treatment, speak with your healthcare provider about whether another course of CHANTIX therapy may be right for you.

What are the ingredients in CHANTIX?

Active ingredient: varenicline tartrate

Inactive ingredients: microcrystalline cellulose, anhydrous dibasic calcium phosphate, croscarmellose sodium, colloidal silicon dioxide, magnesium stearate, Opadry® White (for 0.5 mg), Opadry® Blue (for 1 mg), and Opadry® Clear.

LAB-0328-18.0

This Medication Guide has been approved by the U.S. Food and Drug Administration. Revised: 6/2025

PRINCIPAL DISPLAY PANEL - 0.5 mg / 1 mg Tablet Starting Pack

NDC 0069-0471-28
Rx only

CHANTIX®
(varenicline) TABLETS

STARTING PACK

Use the Starting Week (green) blister card
first when beginning to take Chantix.

Contains:
1 Starting Week (0.5 mg* x 11 tablets)
3 Continuing Weeks (1 mg† x 42 tablets)

ALWAYS DISPENSE WITH ENCLOSED MEDICATION GUIDE

PRINCIPAL DISPLAY PANEL - 0.5 mg Tablet Bottle Label

ALWAYS DISPENSE WITH MEDICATION
GUIDE
NDC 0069-0468-56

Pfizer

Chantix®
(varenicline) tablets

0.5 mg*

56 Tablets
Rx only

PRINCIPAL DISPLAY PANEL - 1 mg Tablet Bottle Label

ALWAYS DISPENSE WITH MEDICATION
GUIDE
NDC 0069-0469-56

Pfizer

Chantix®
(varenicline) tablets

1 mg*

56 Tablets
Rx only

PRINCIPAL DISPLAY PANEL - 1 mg x 56 Tablet Continuing Pack

NDC 0069-0469-28
Rx only

CHANTIX®
(varenicline) TABLETS

CONTINUING PACK

Contains:
4 Continuing Weeks (1 mg† x 56 tablets)

ALWAYS DISPENSE WITH ENCLOSED MEDICATION GUIDE